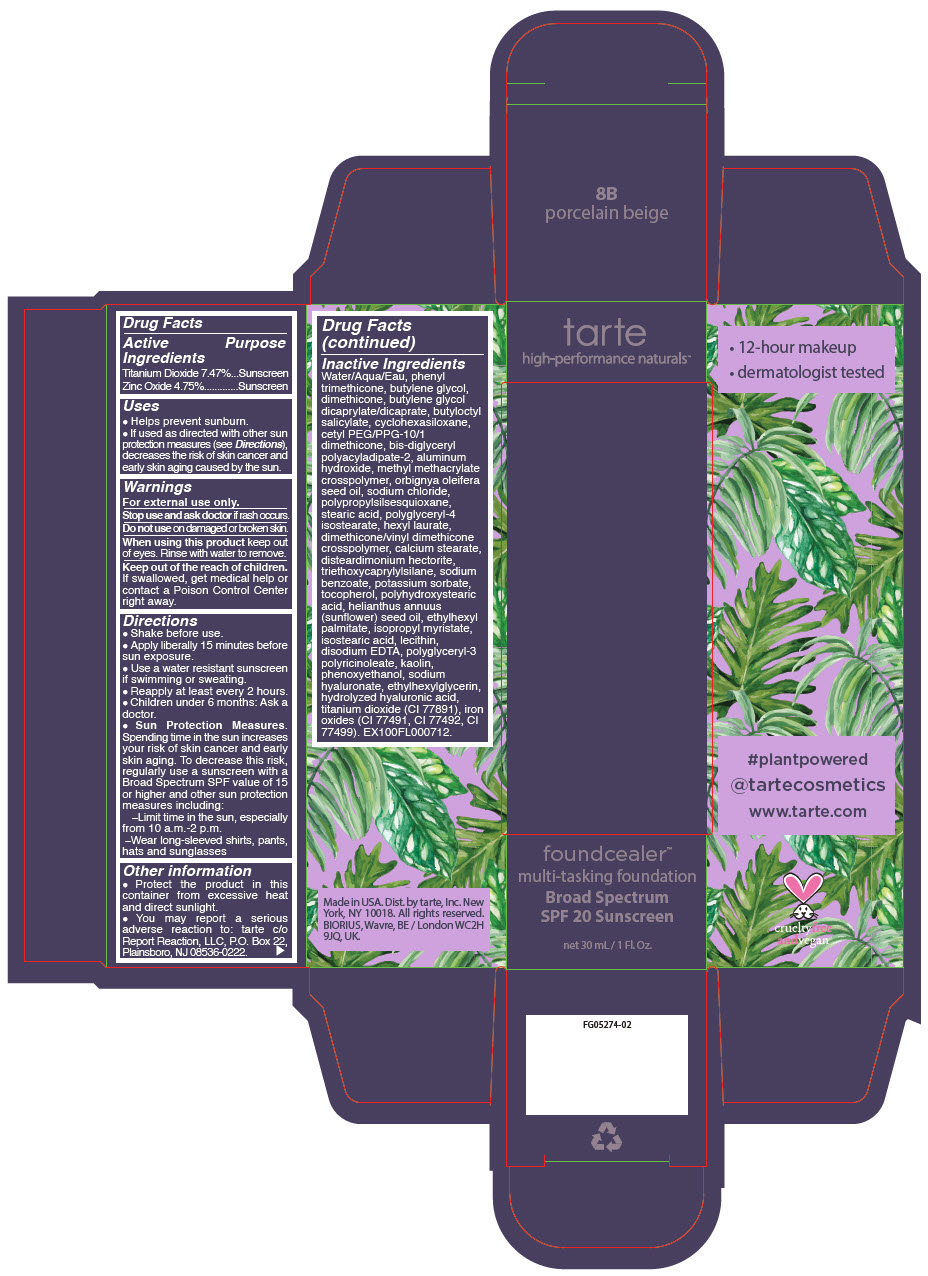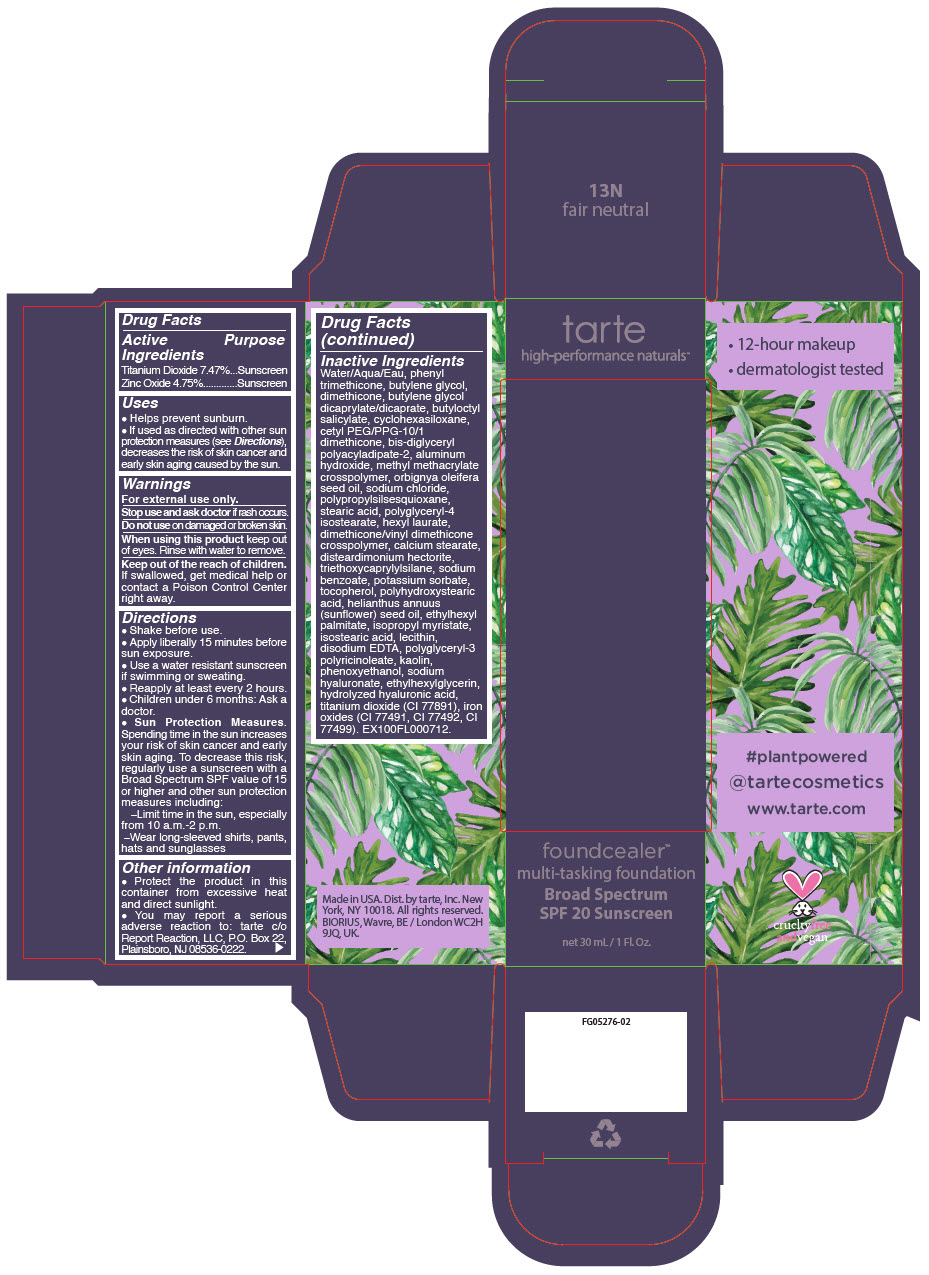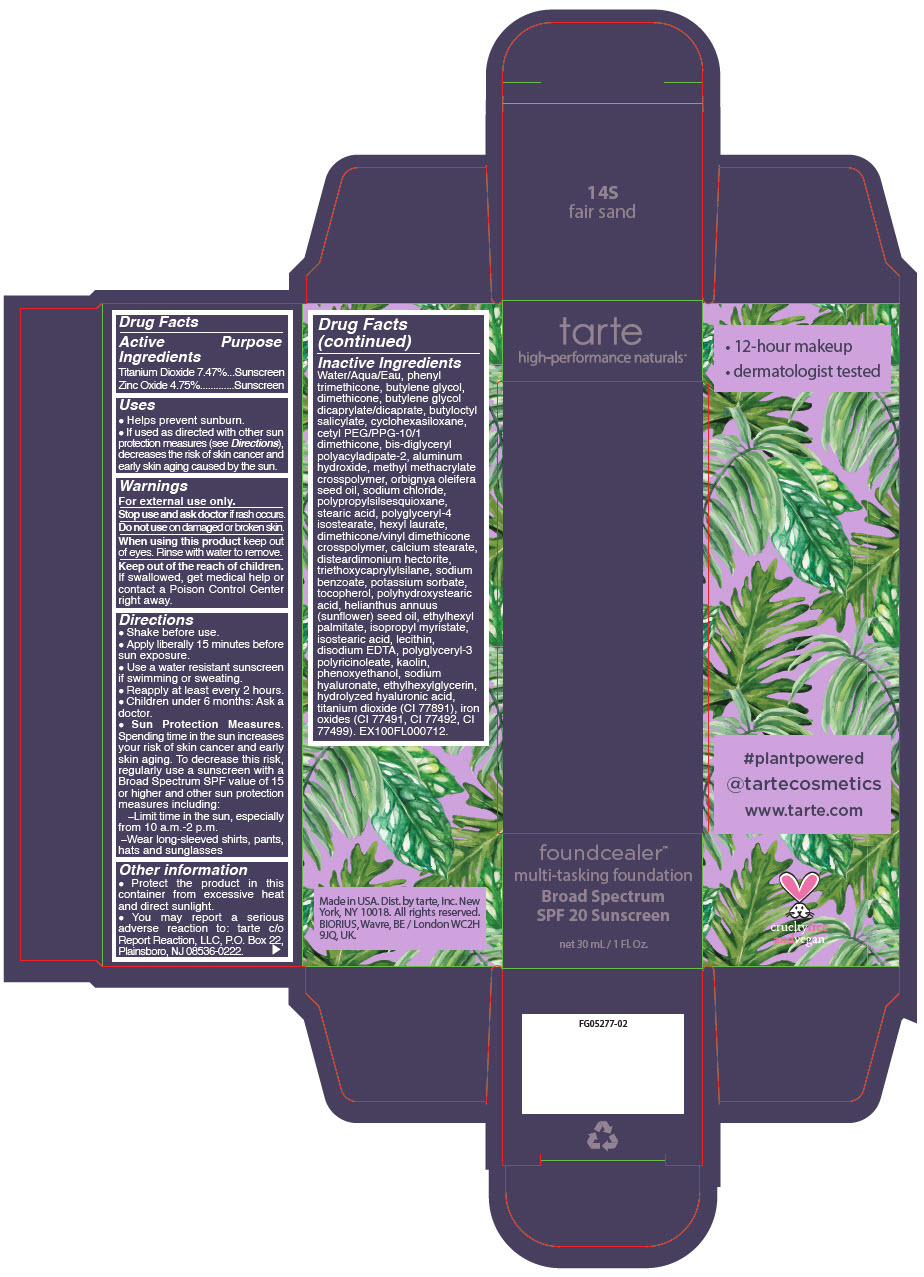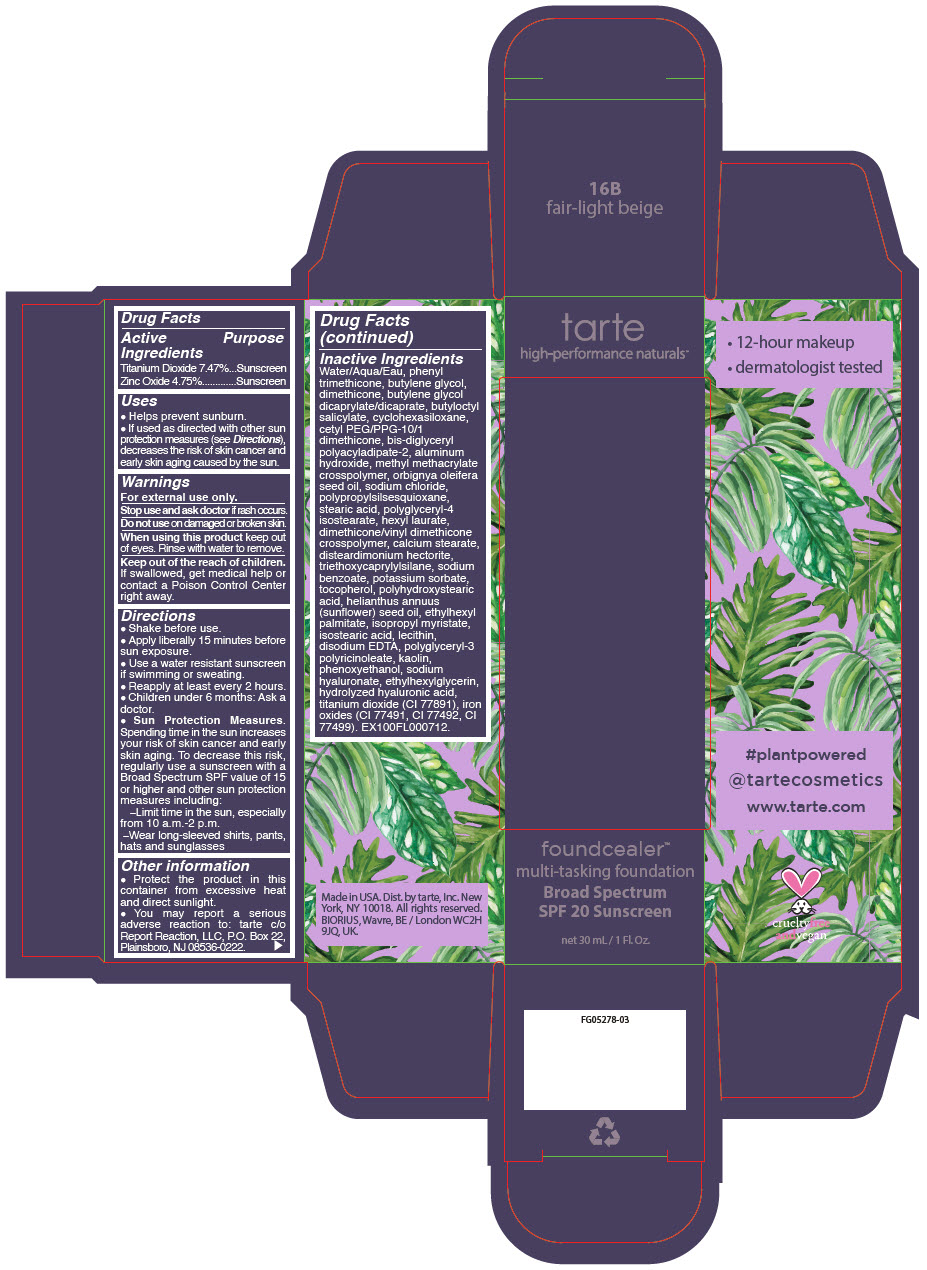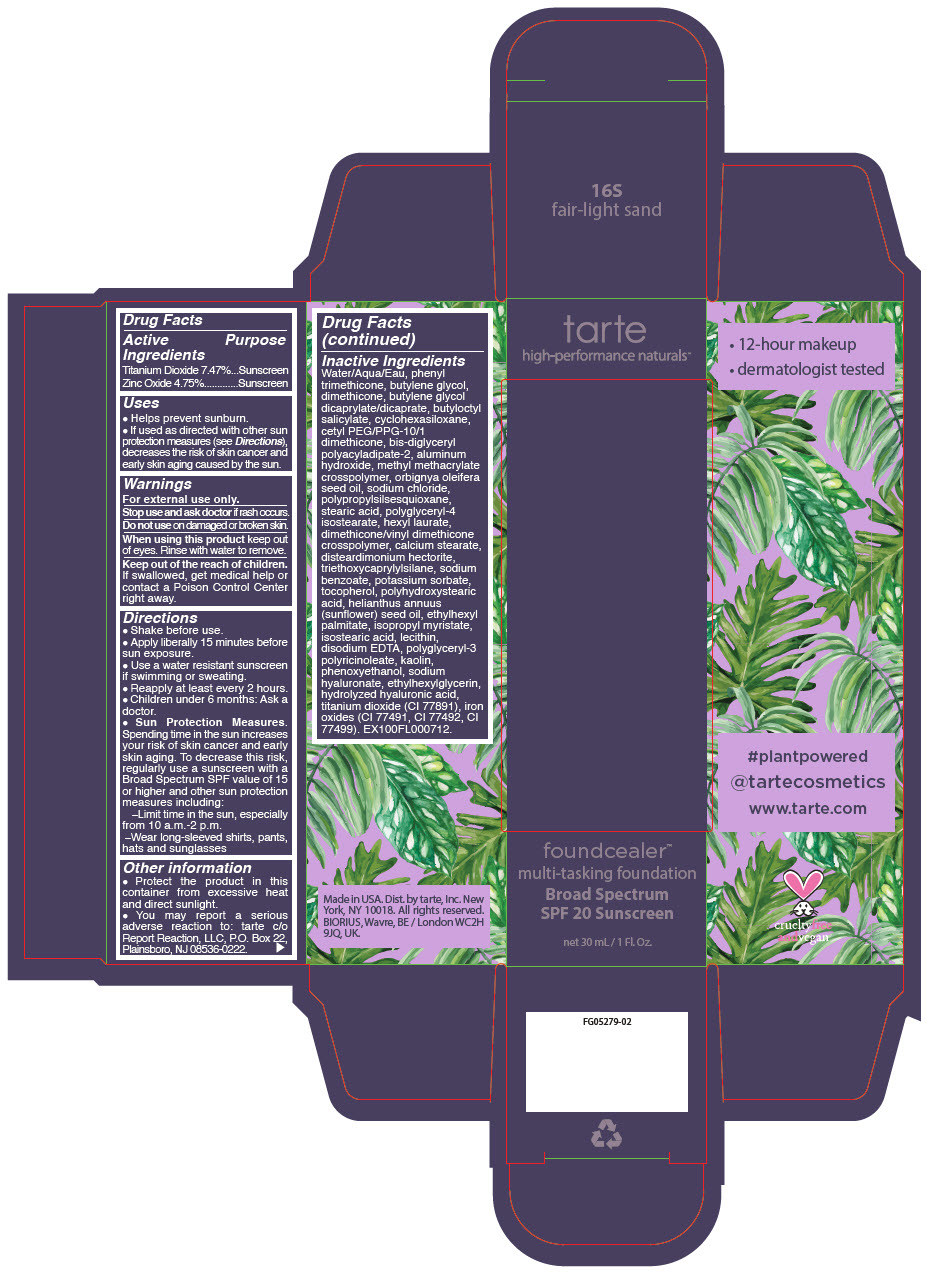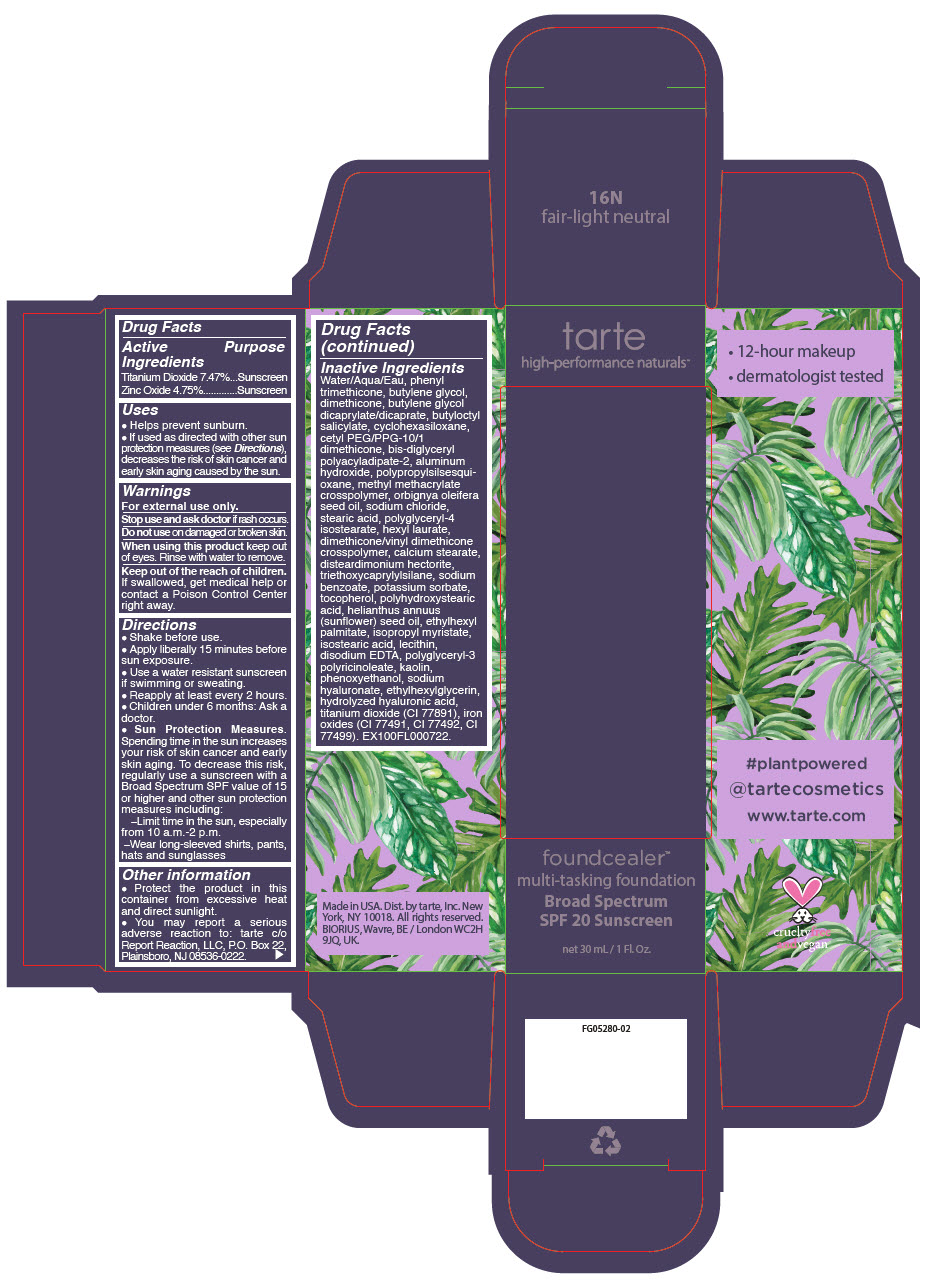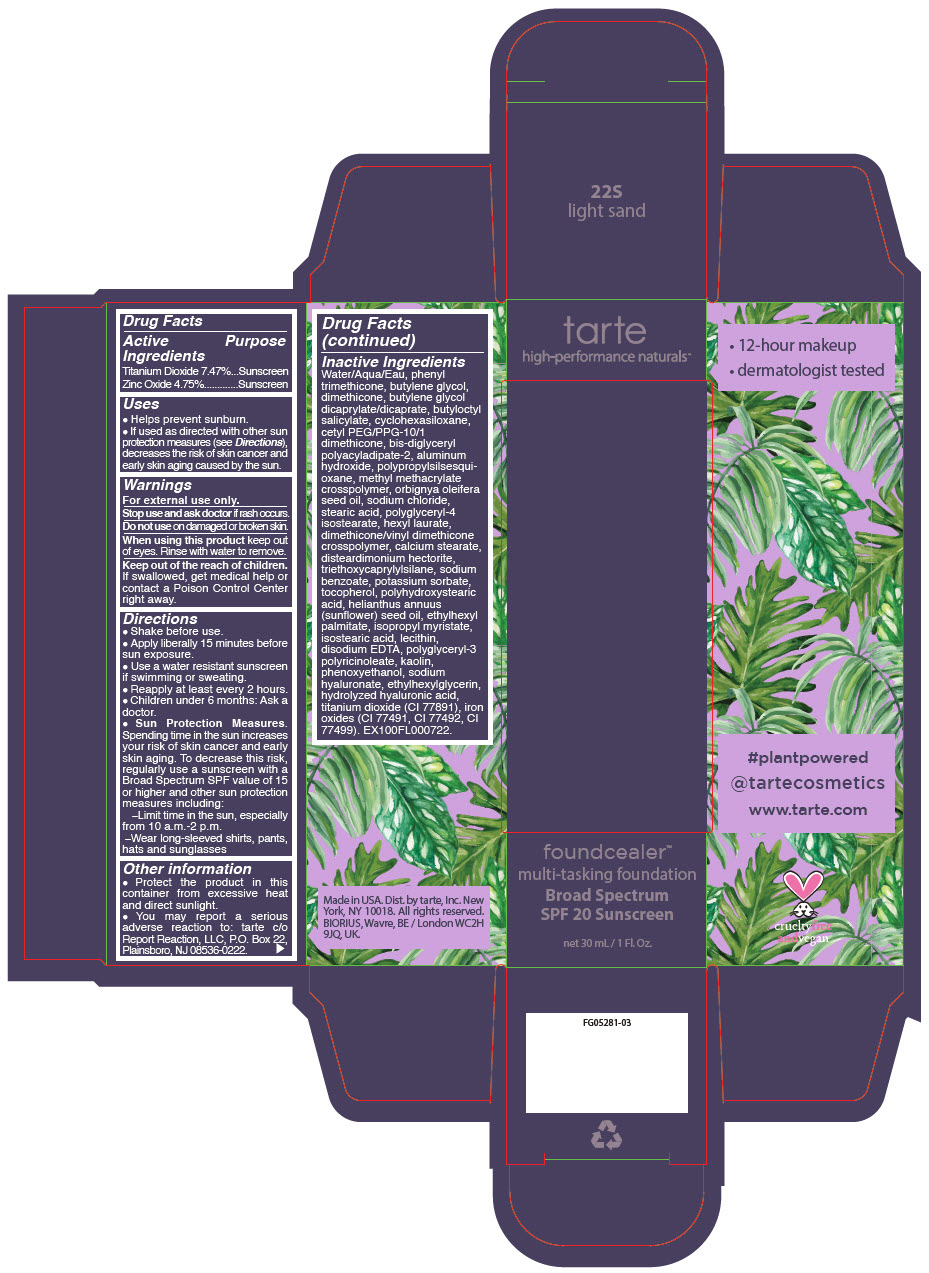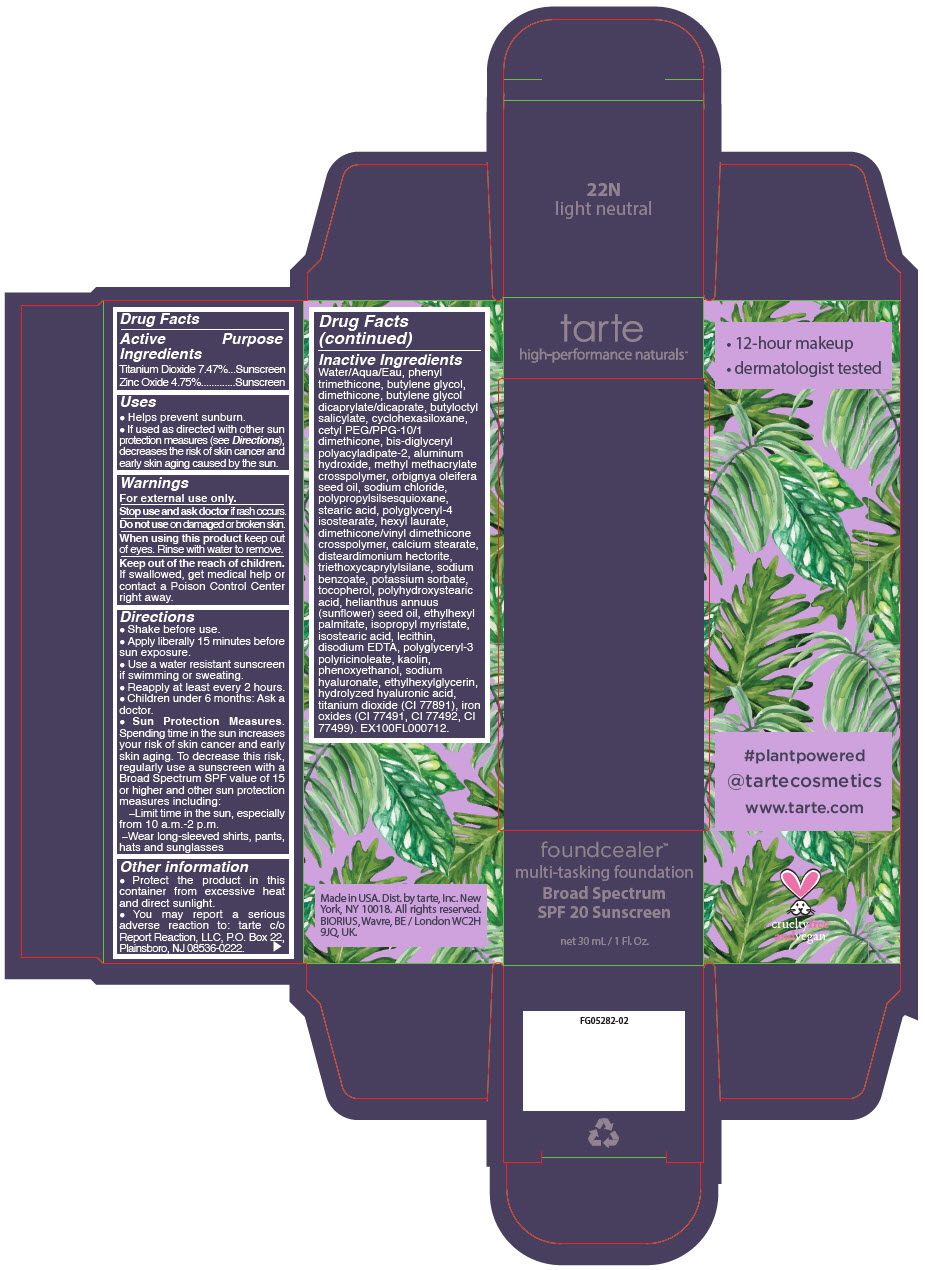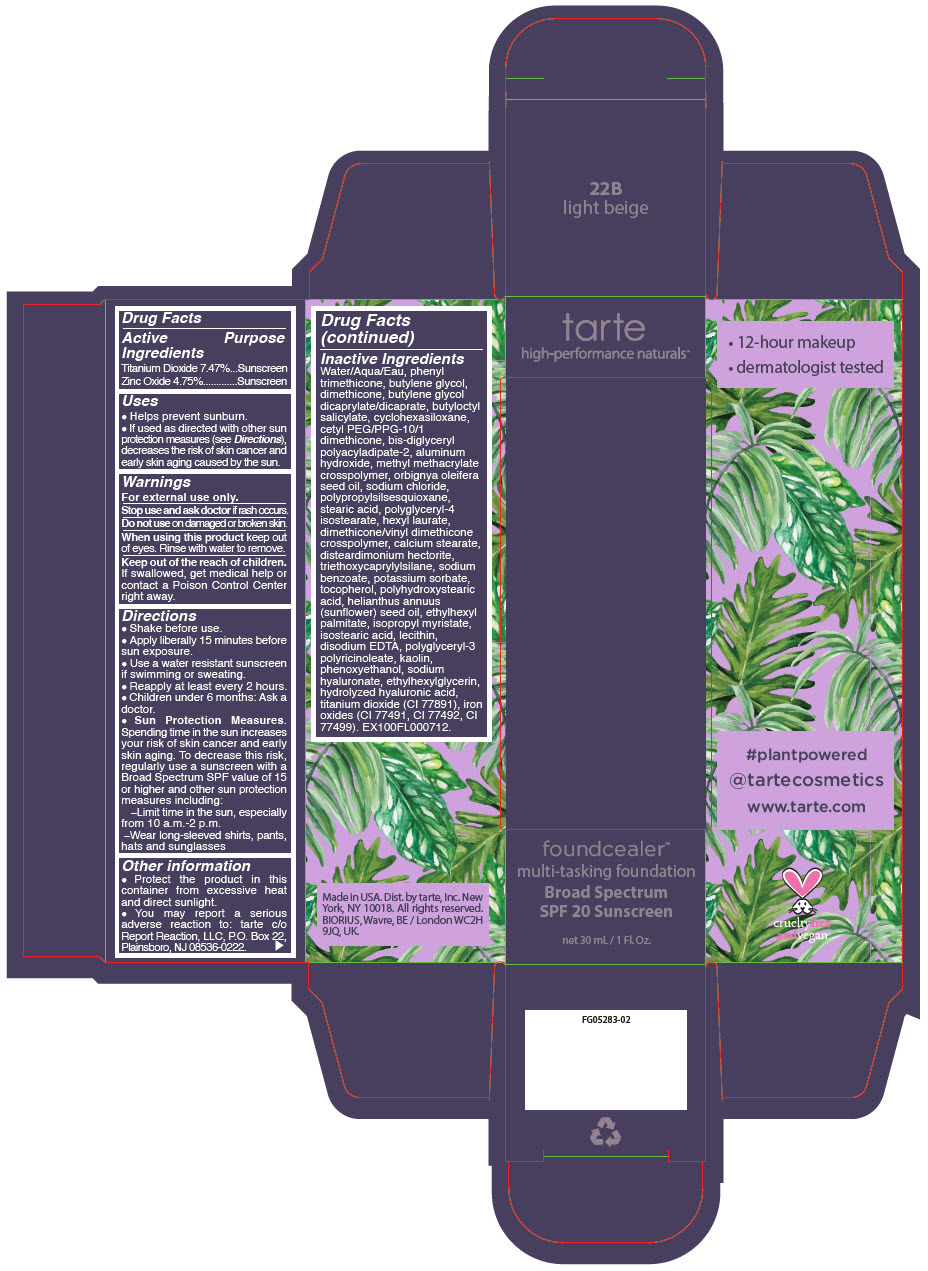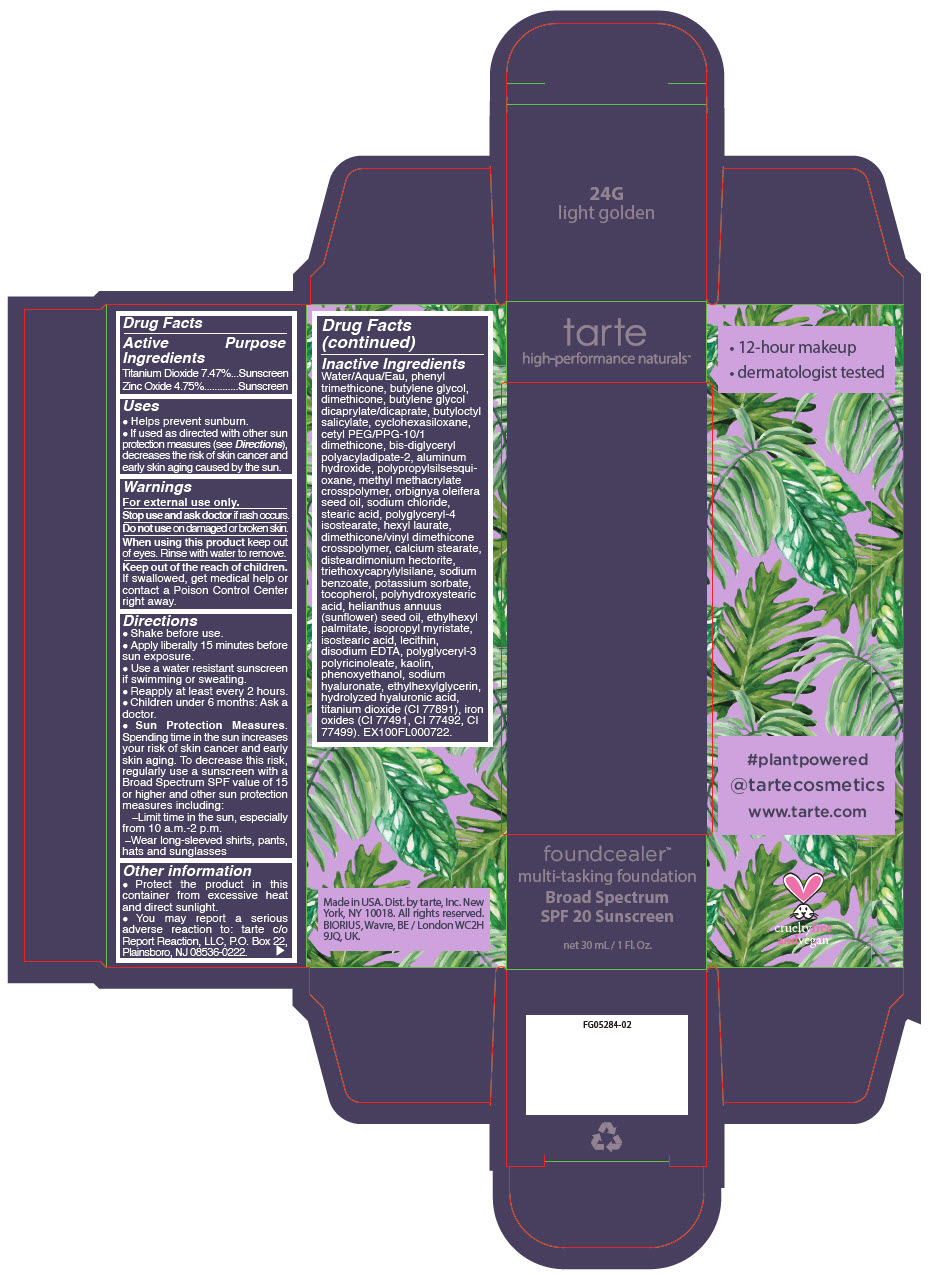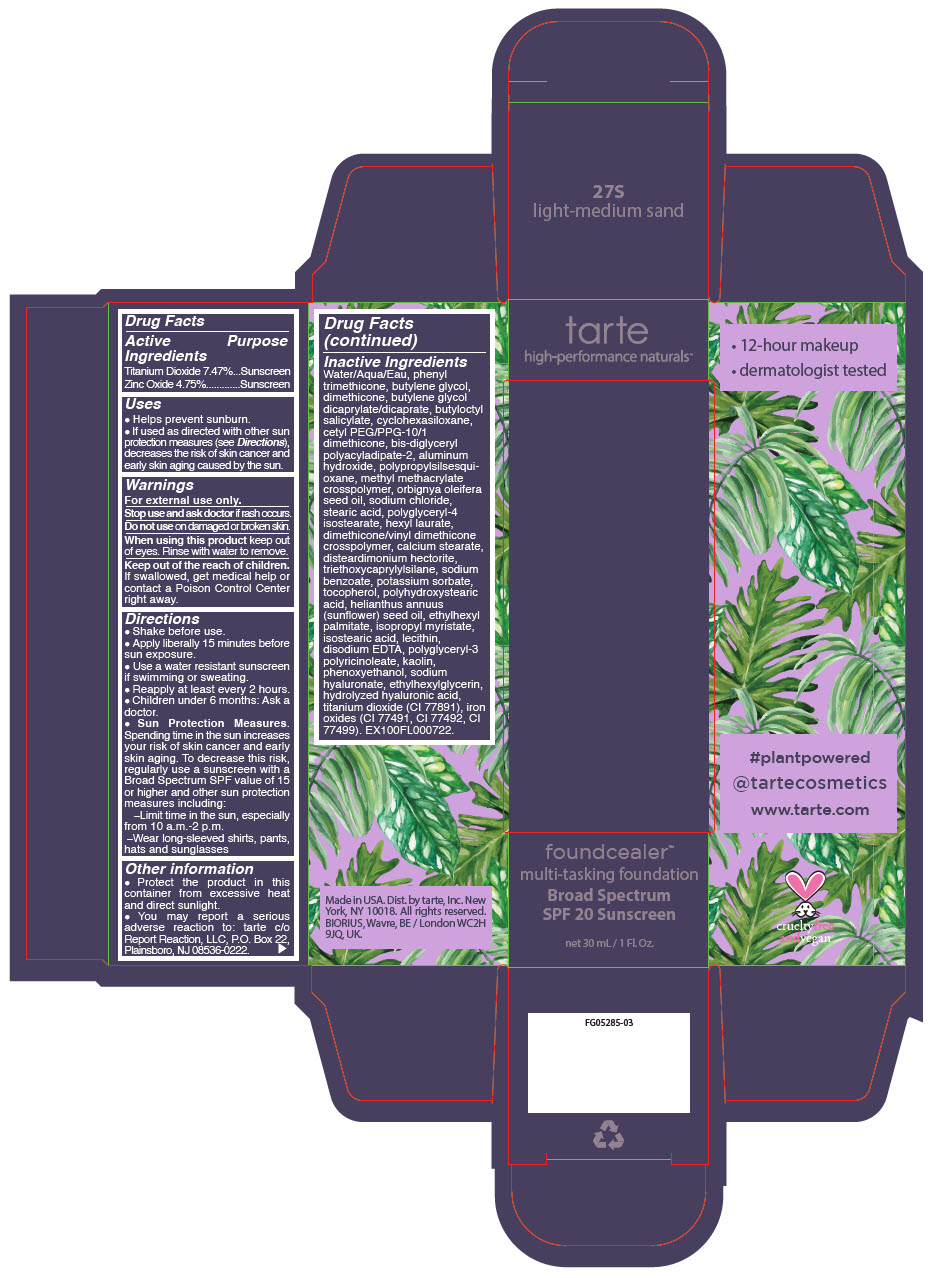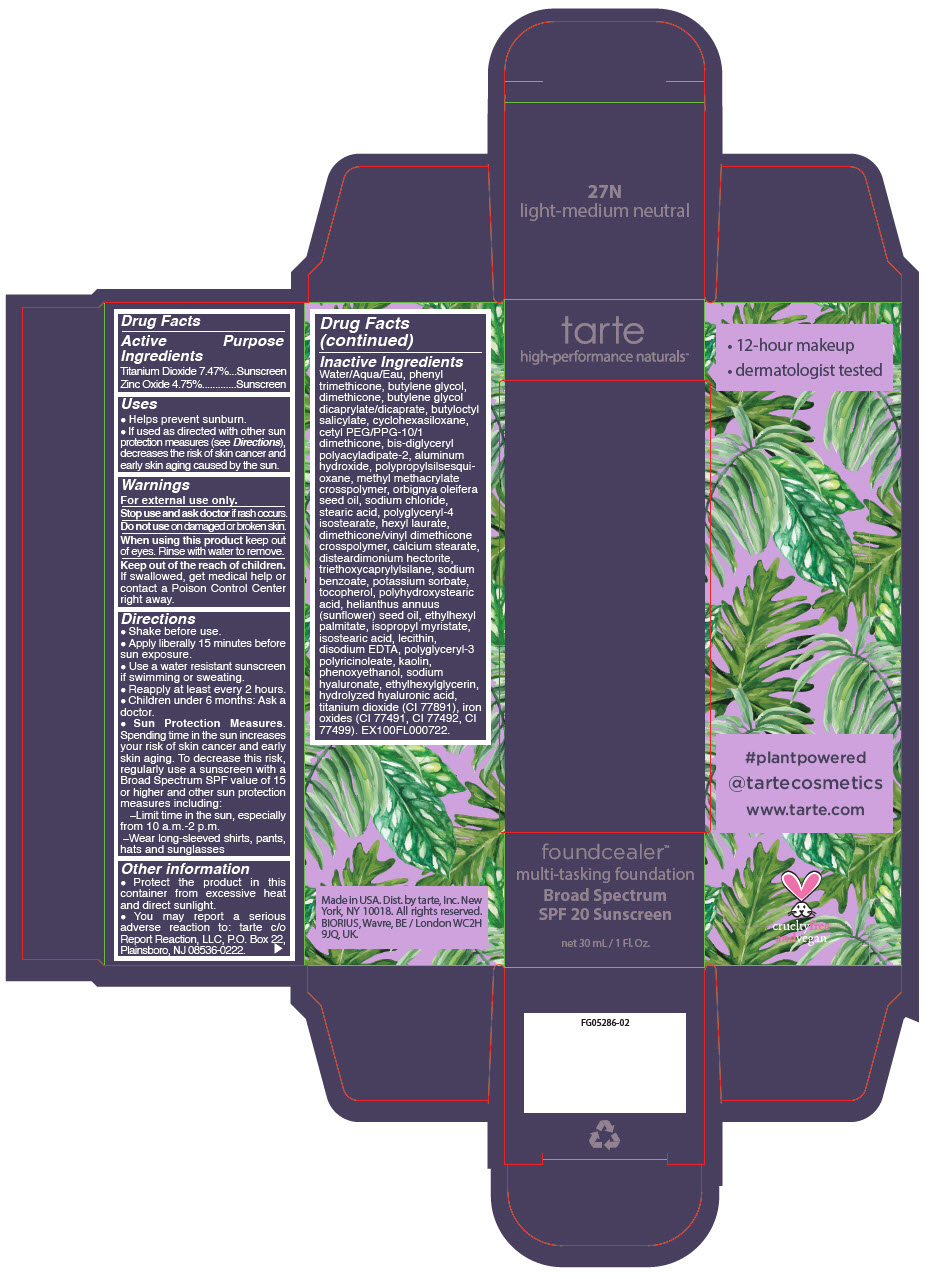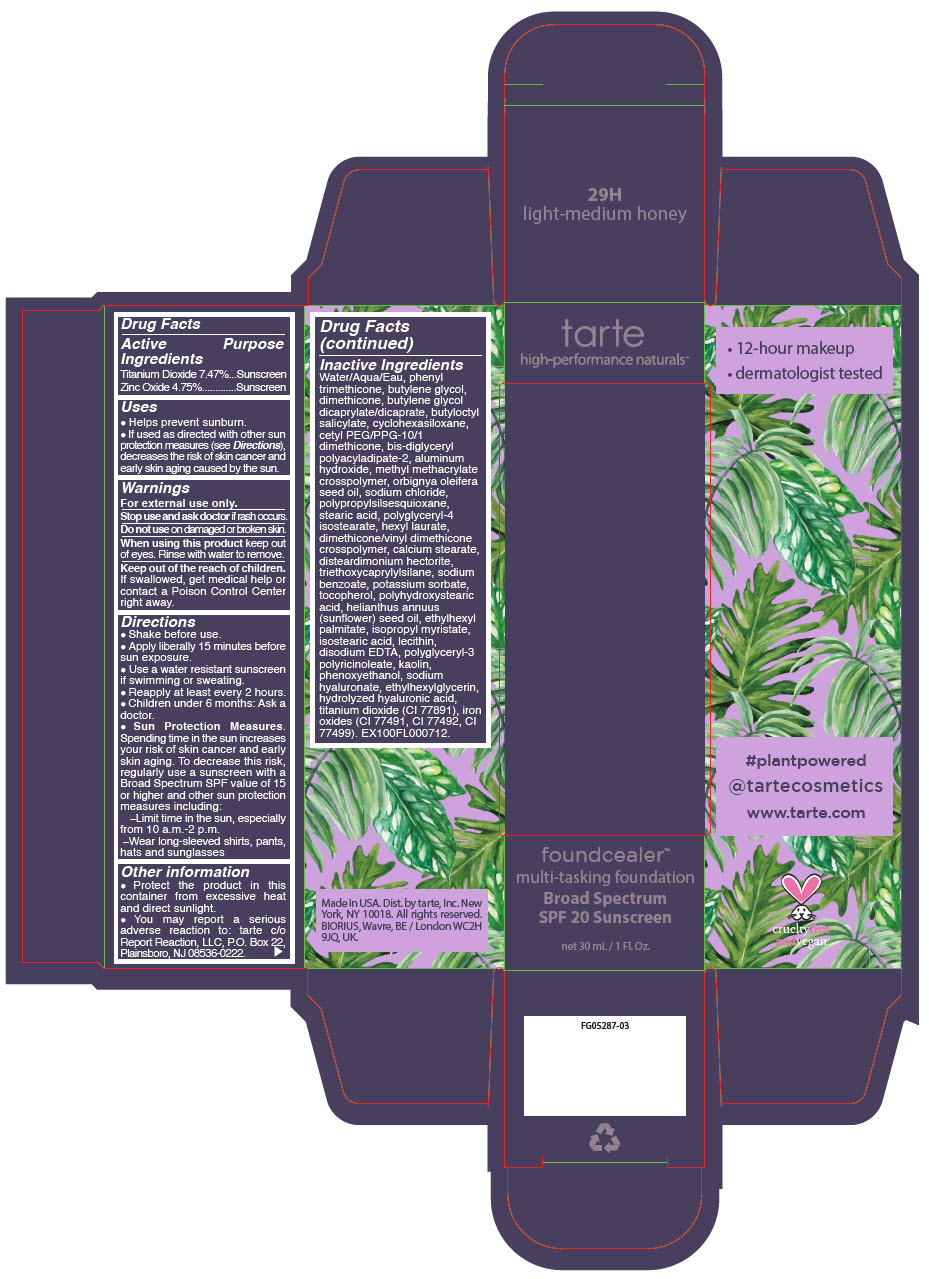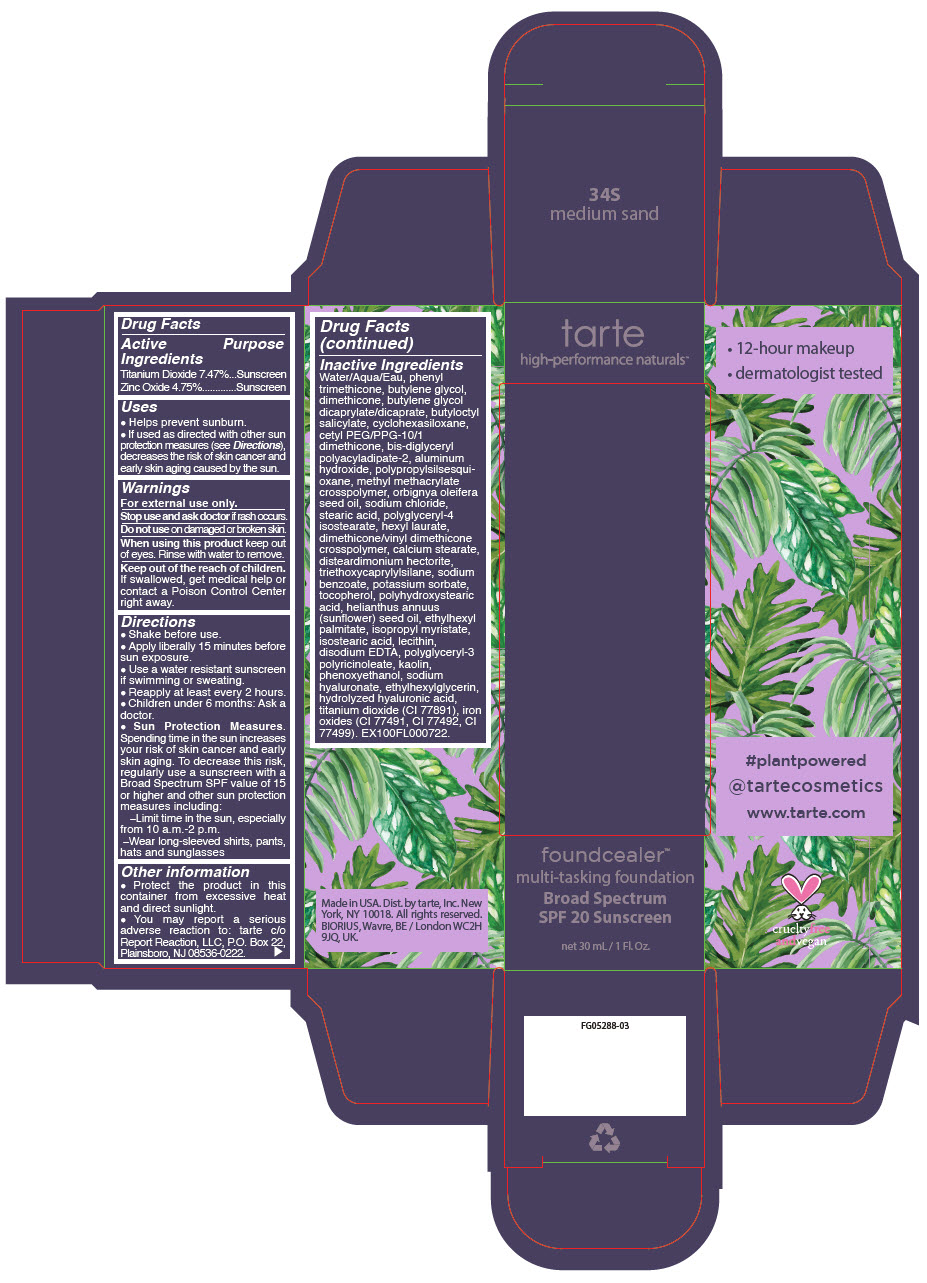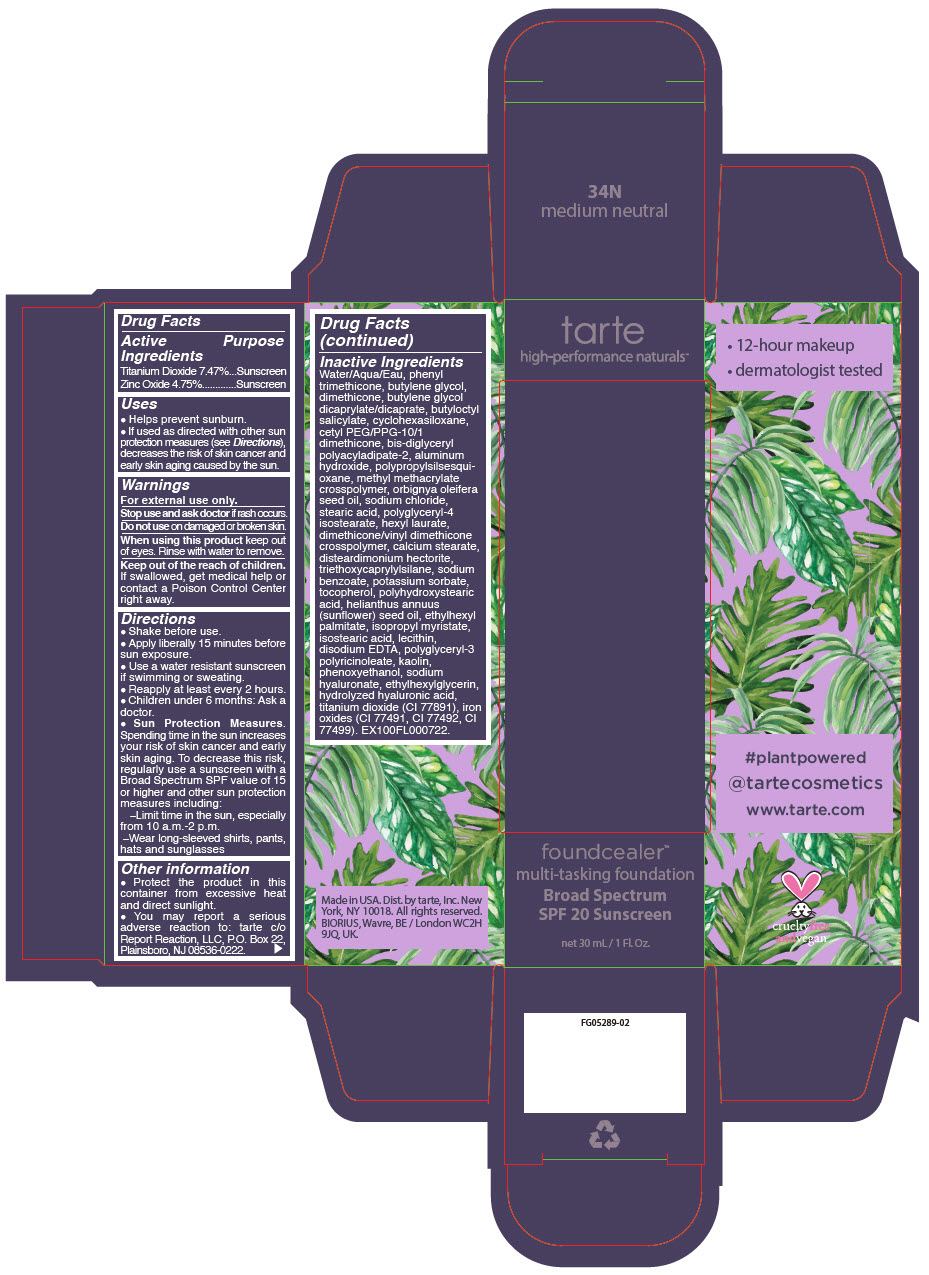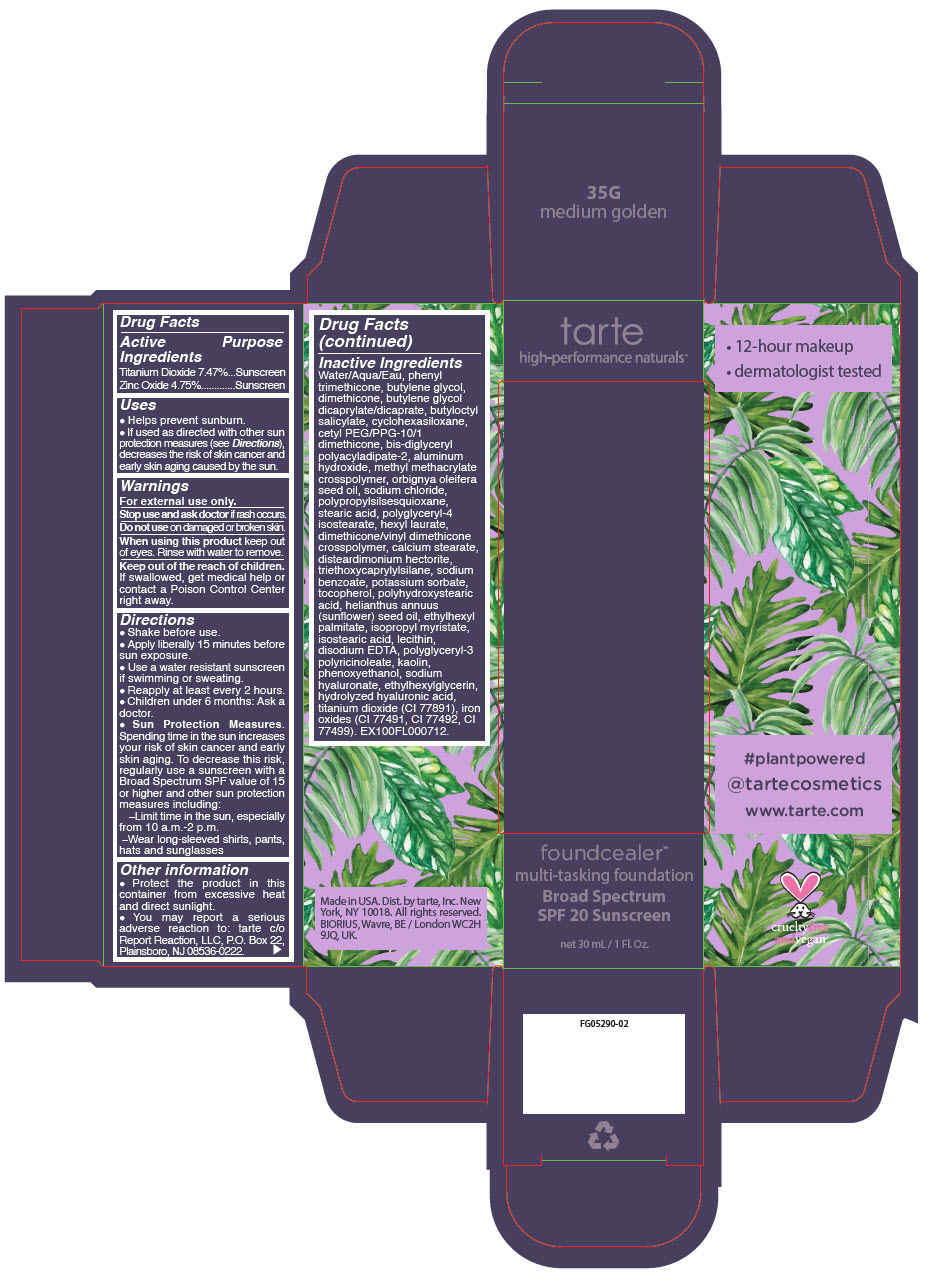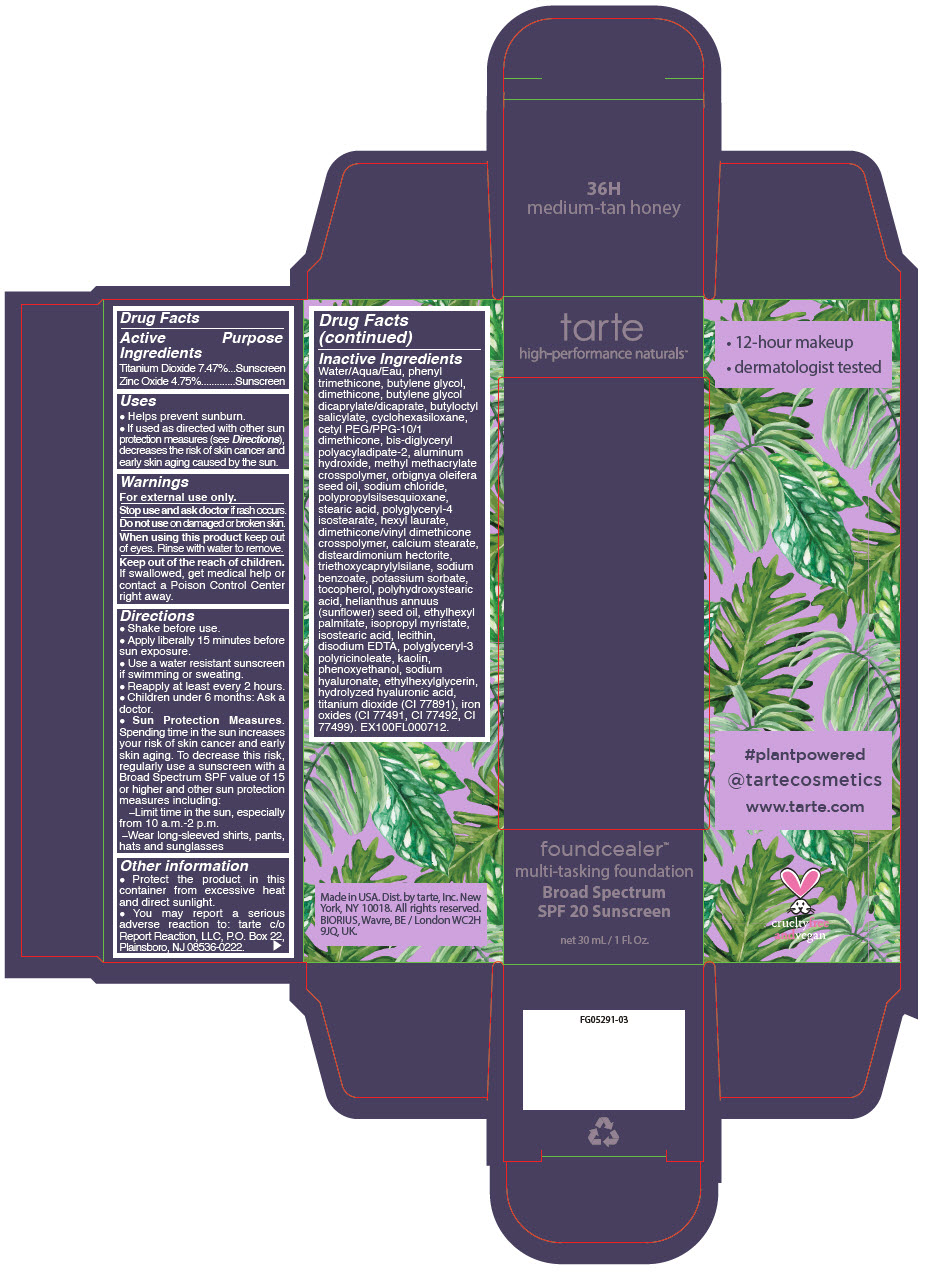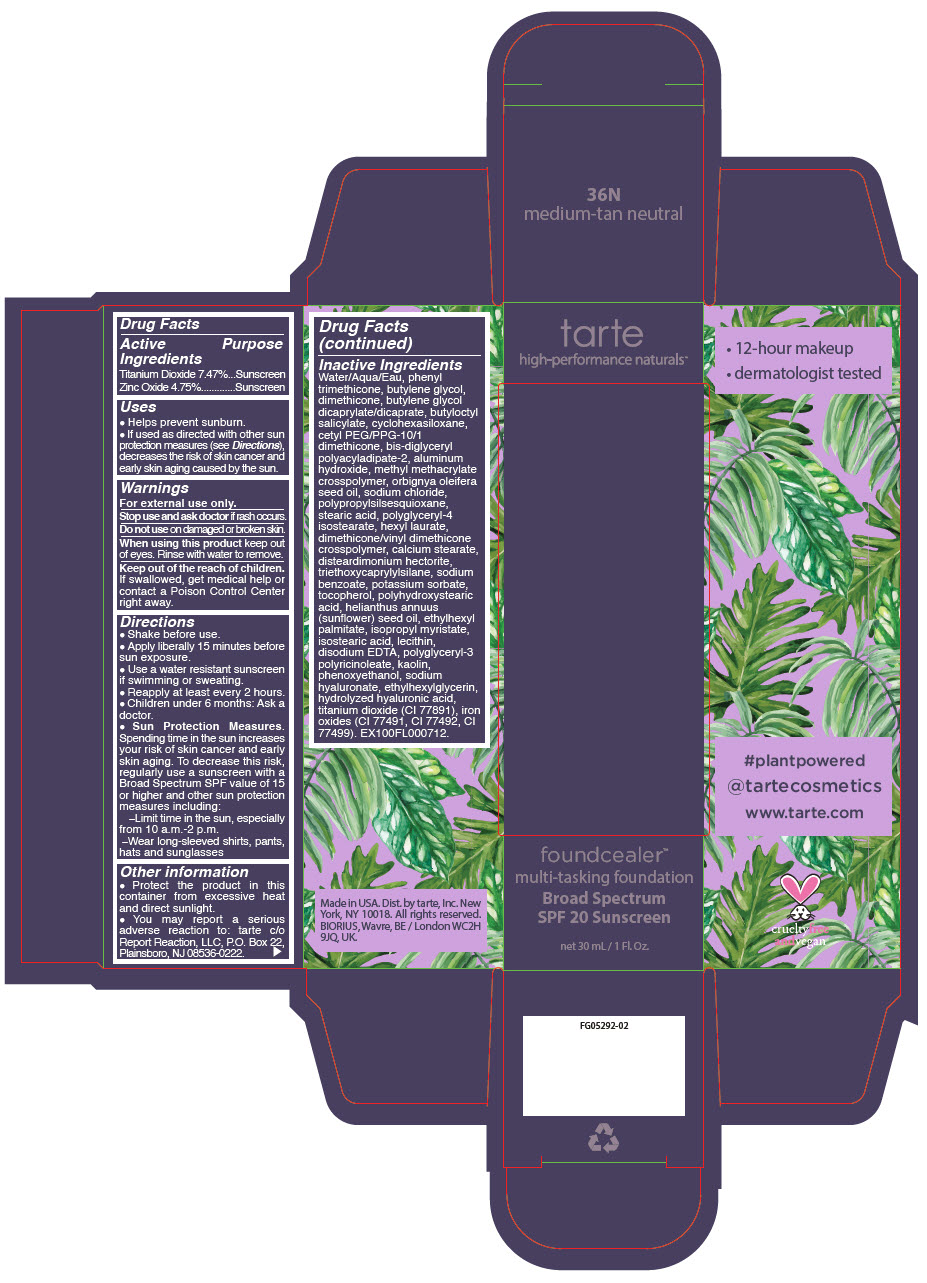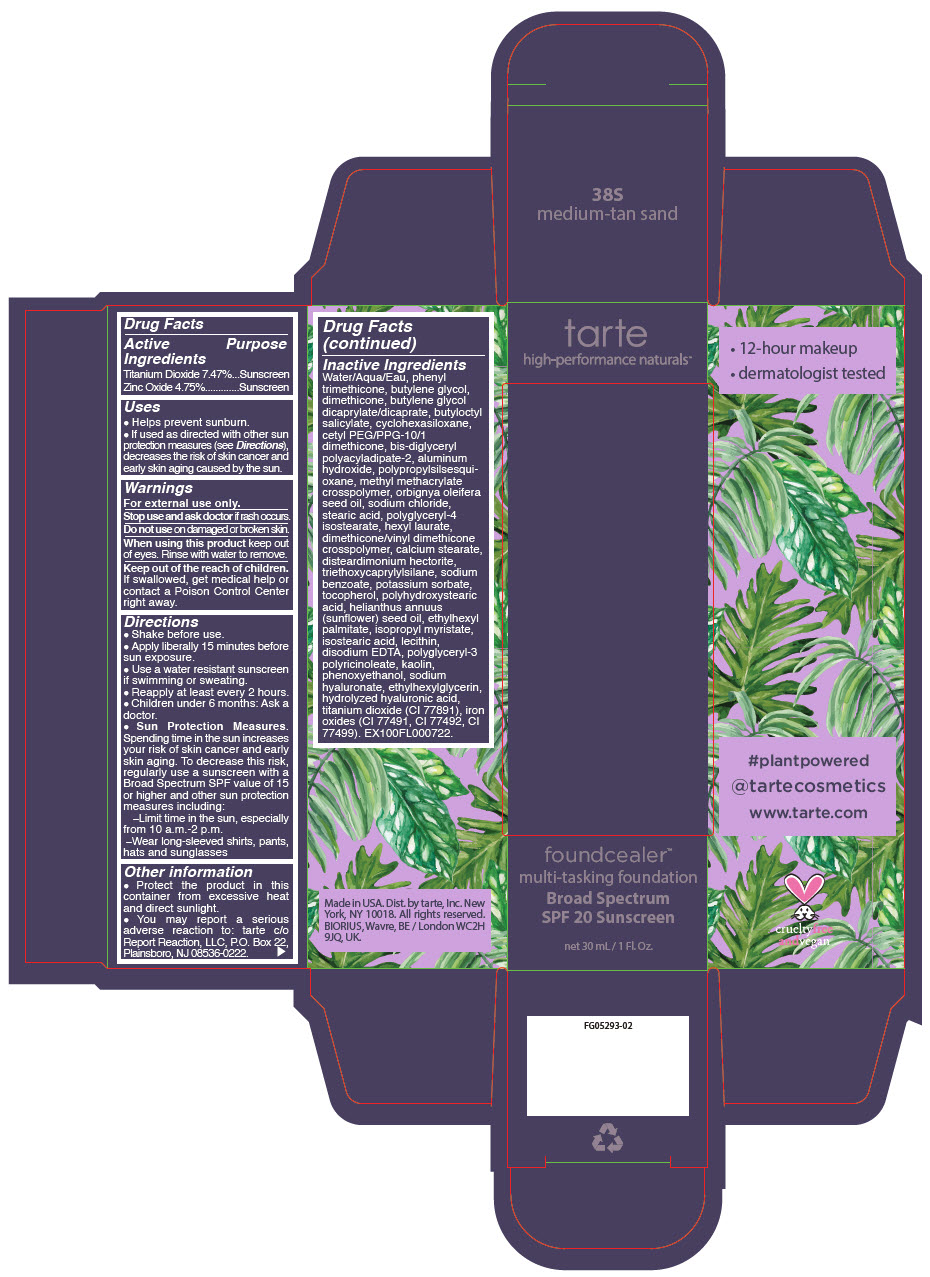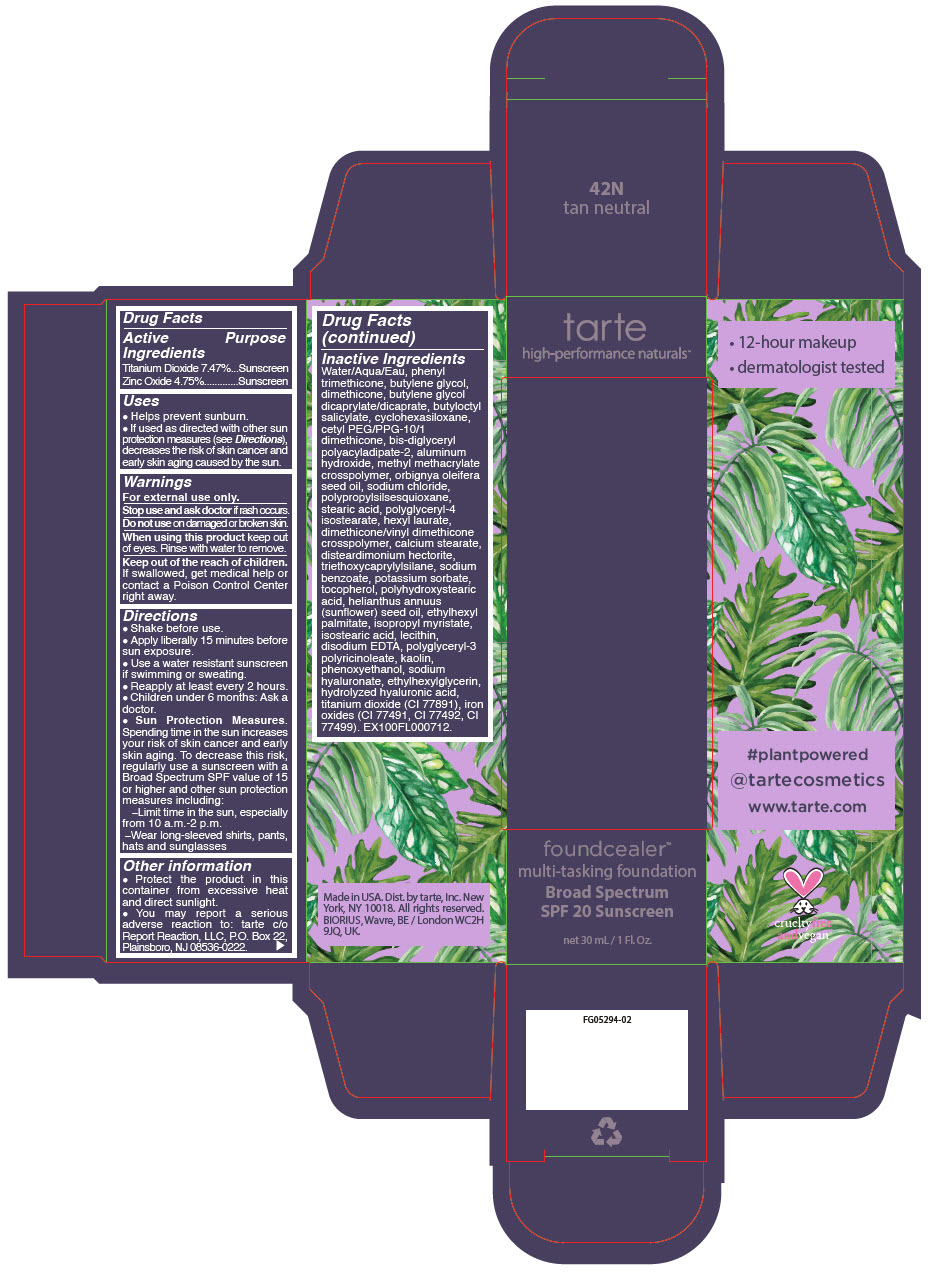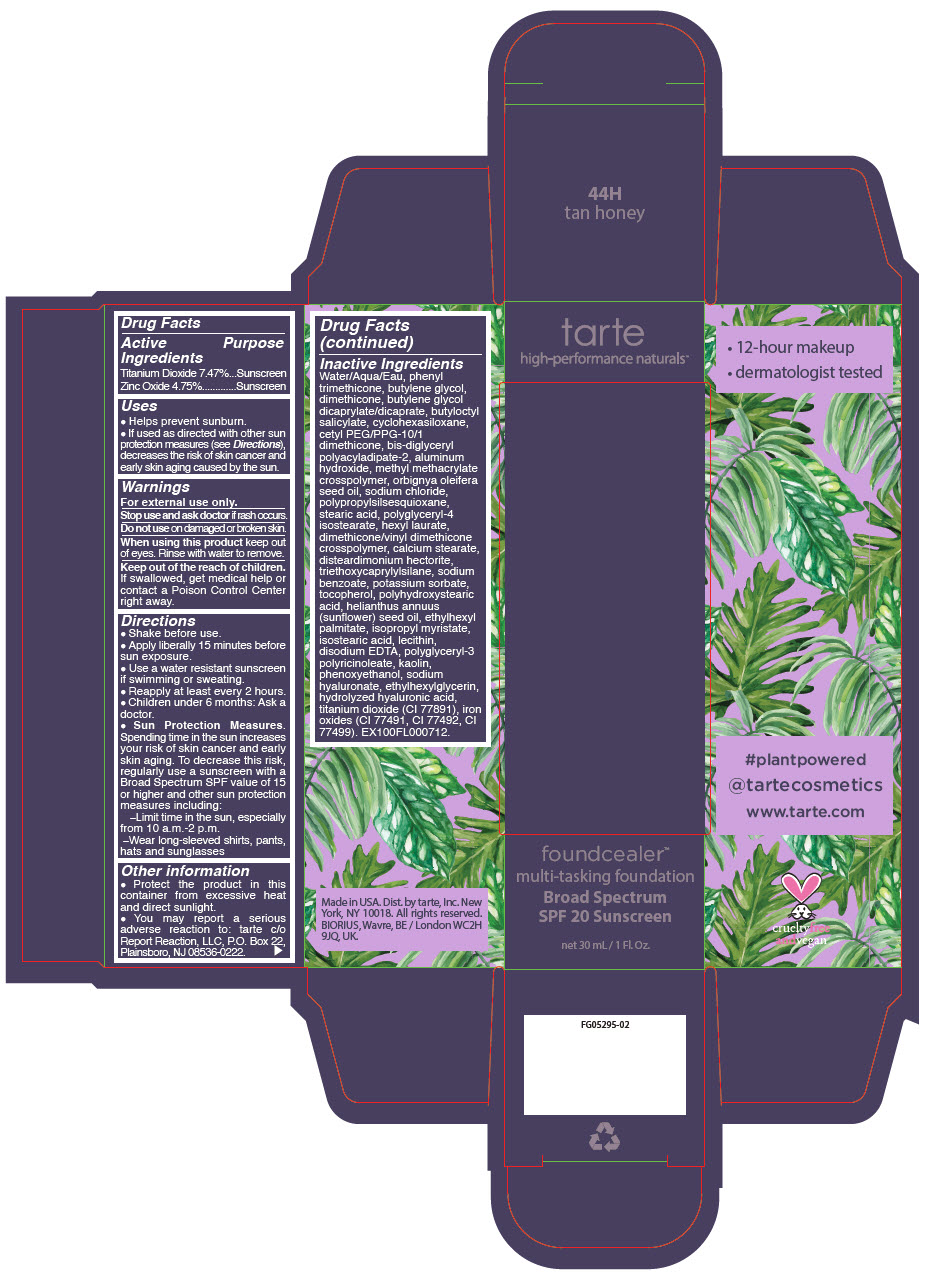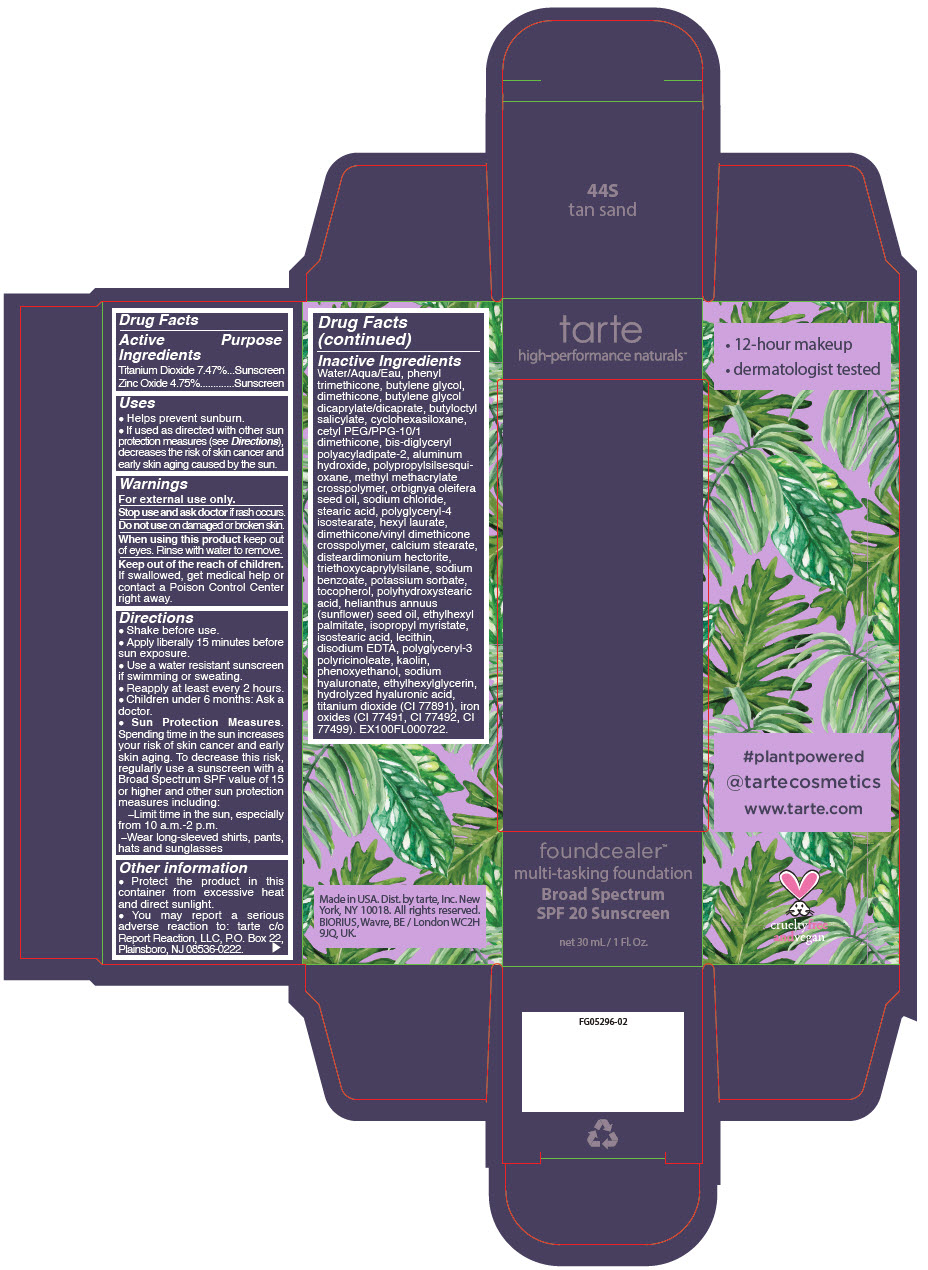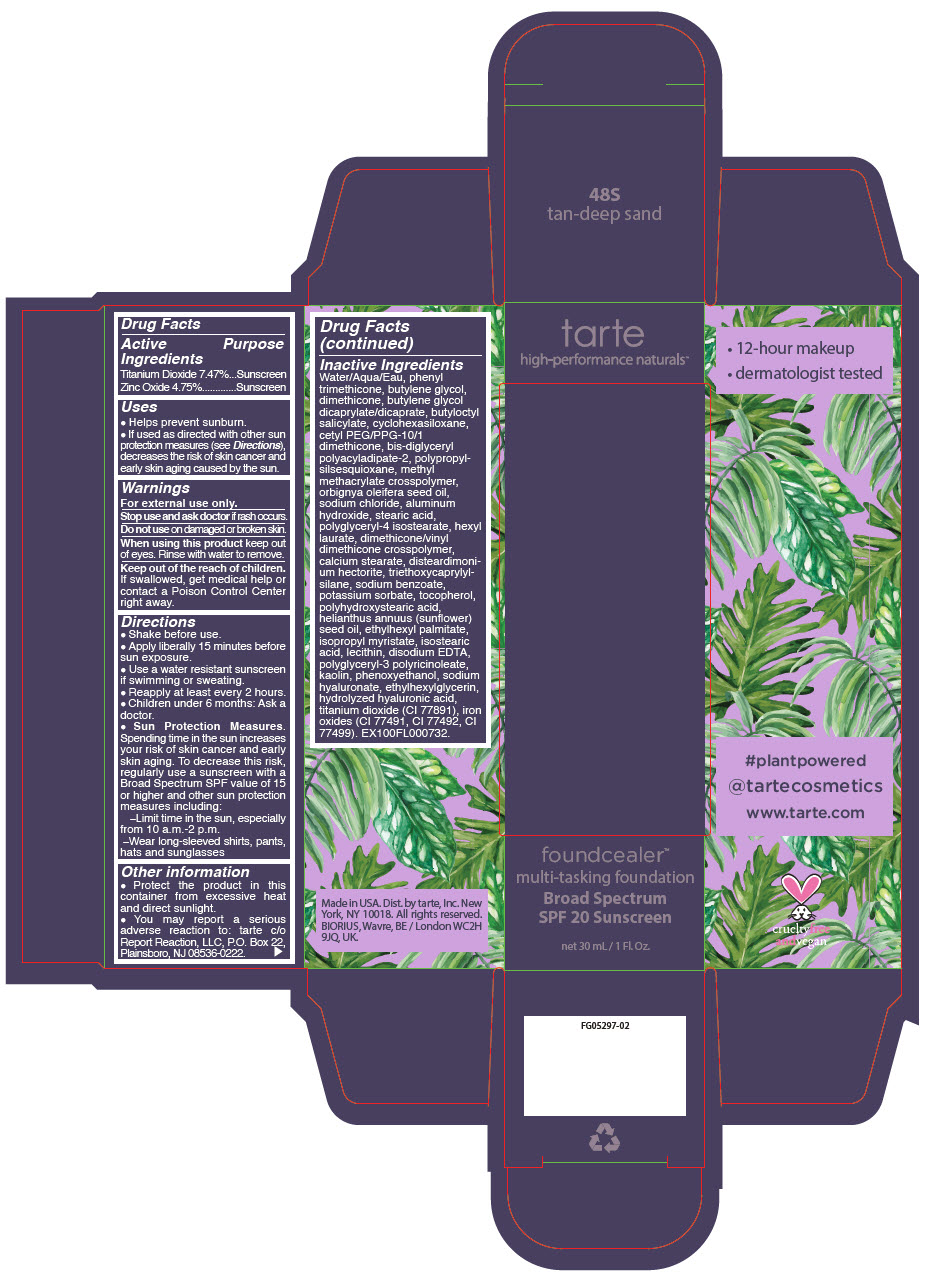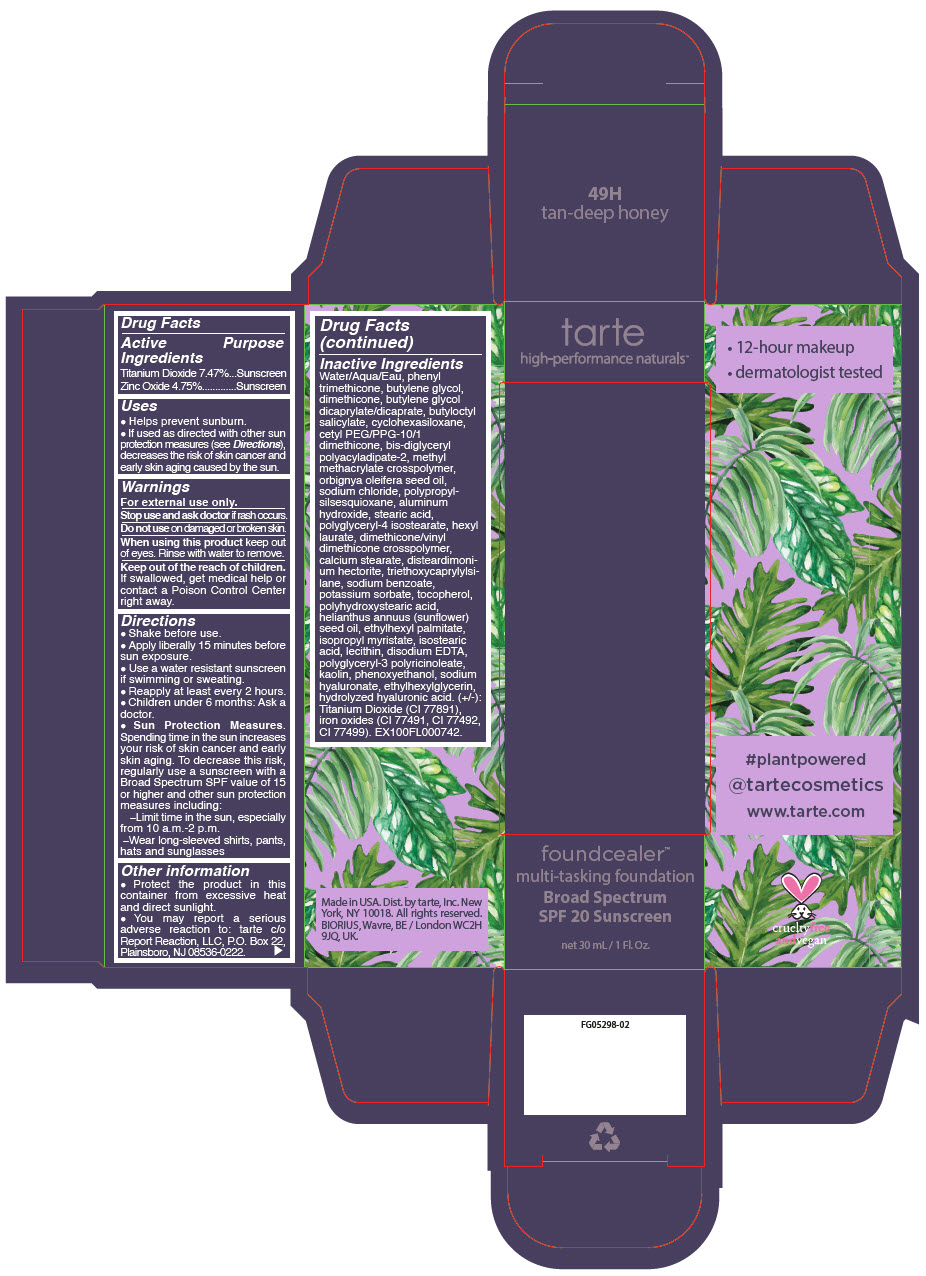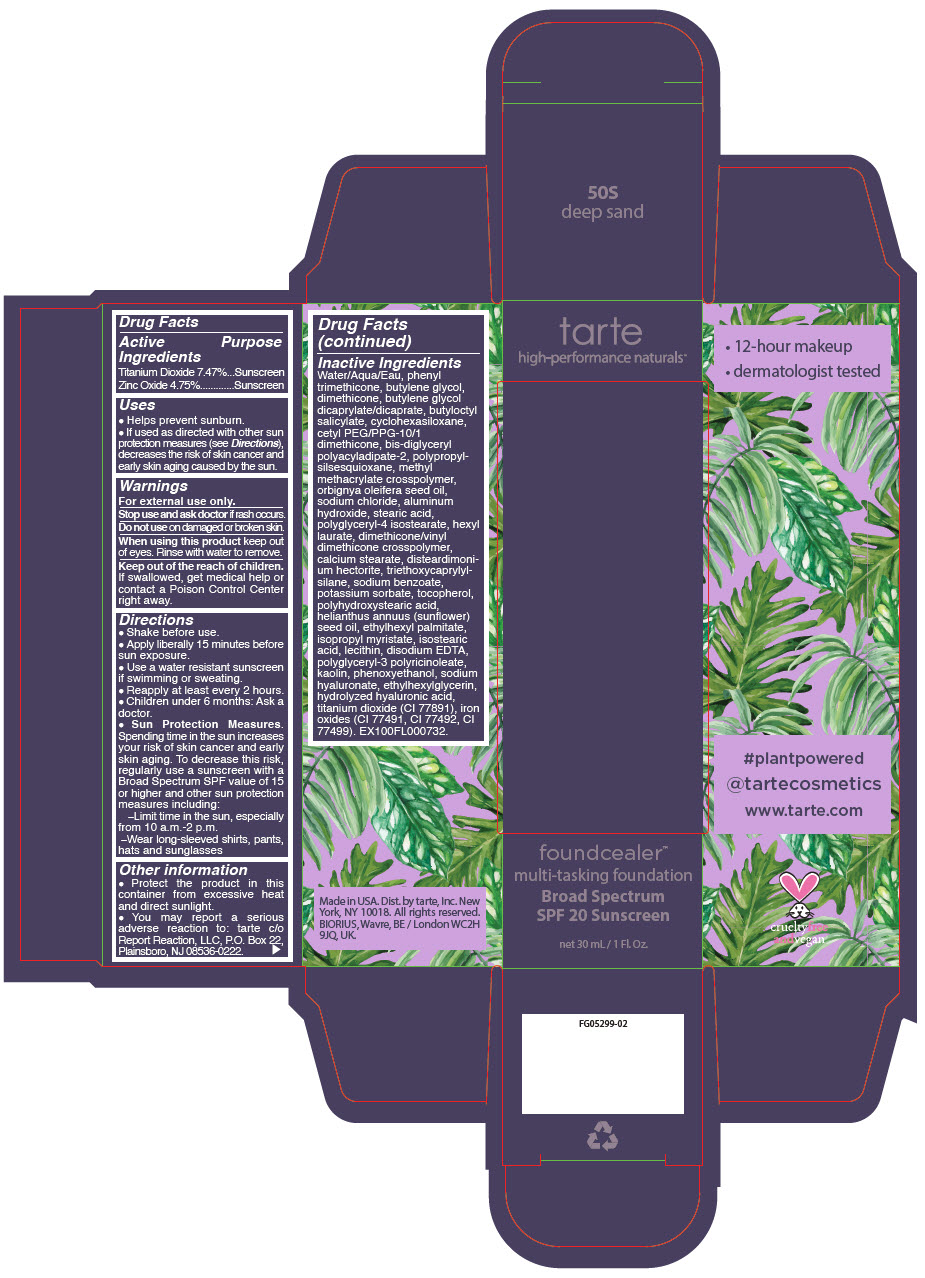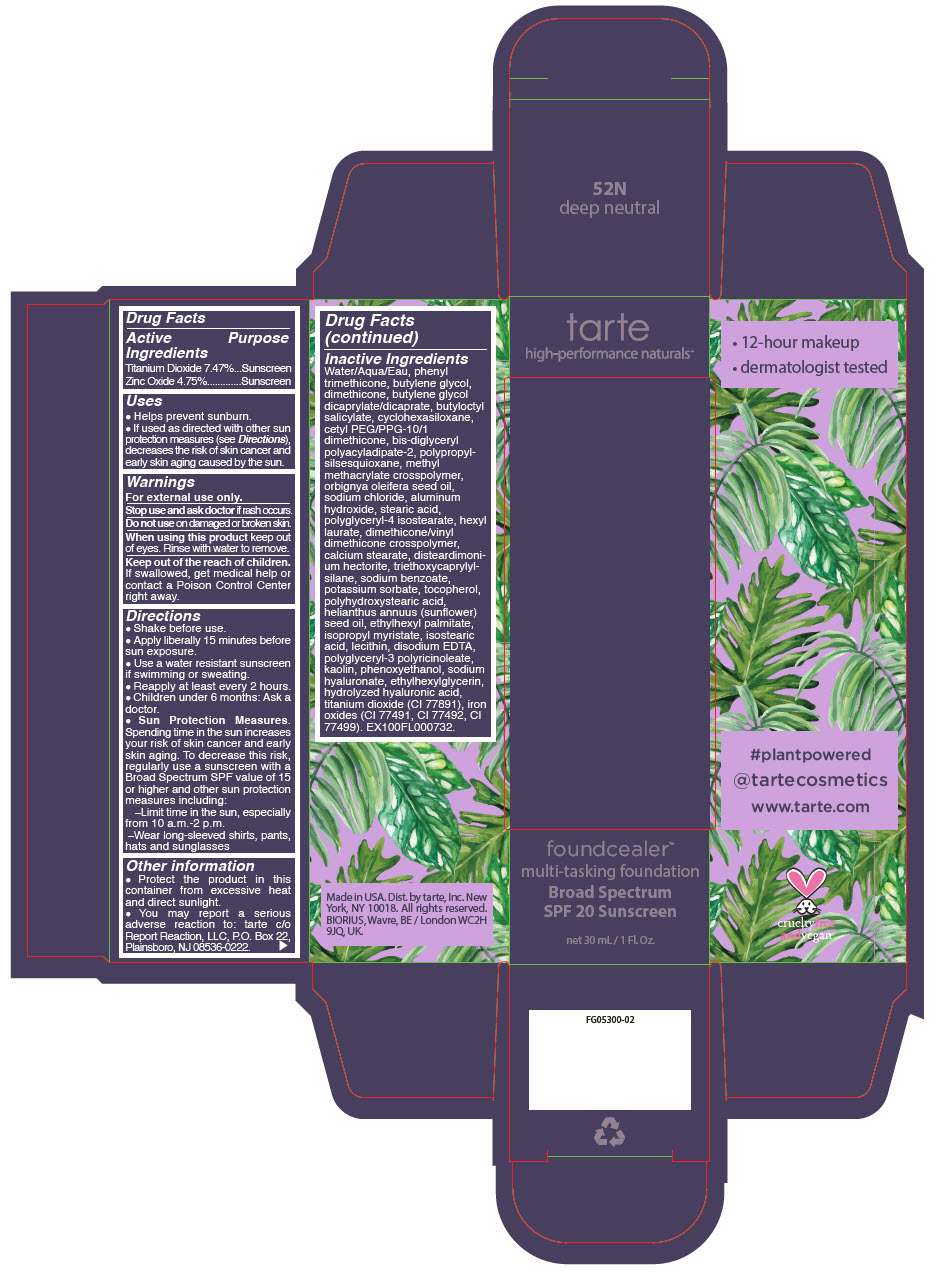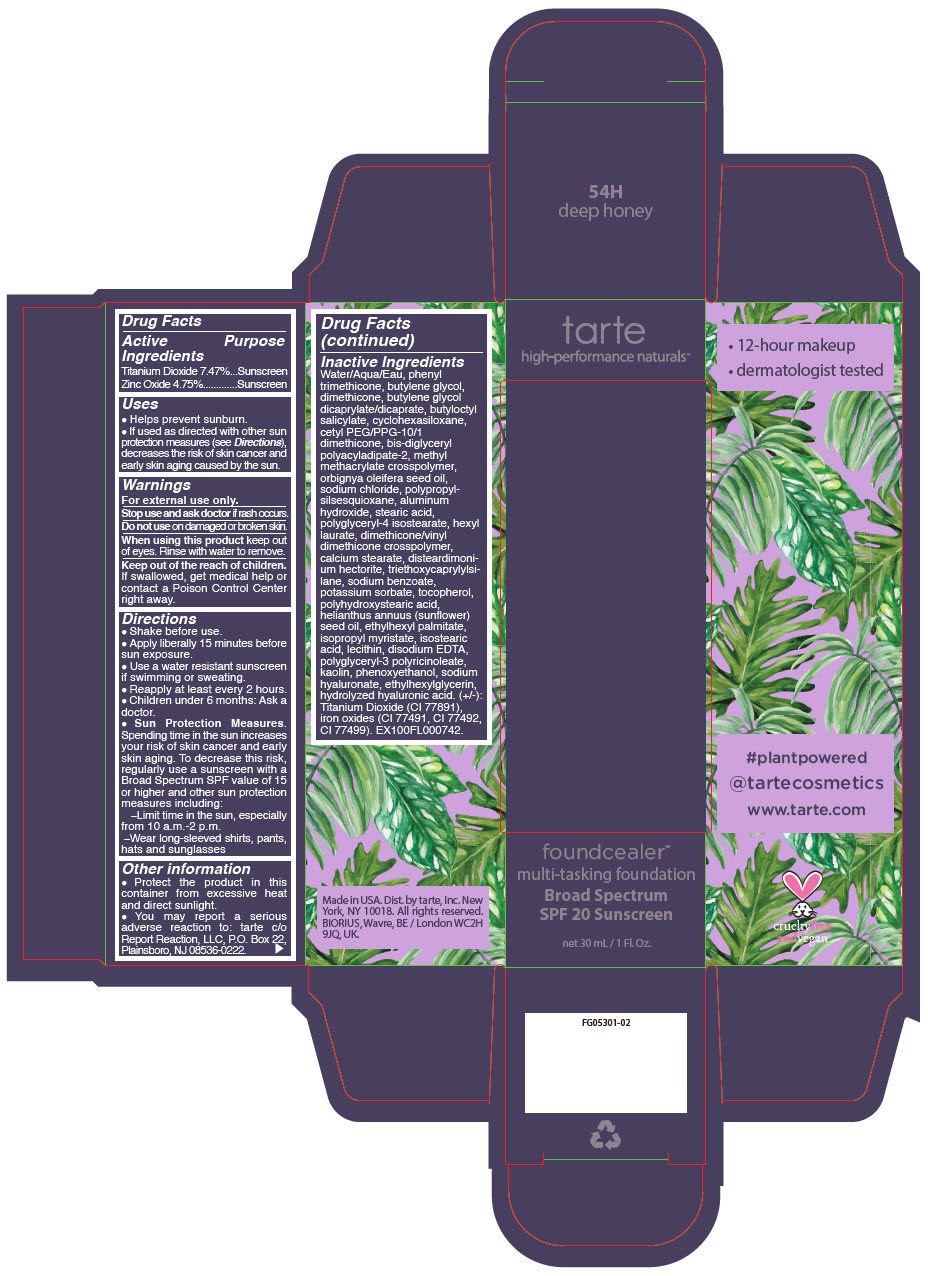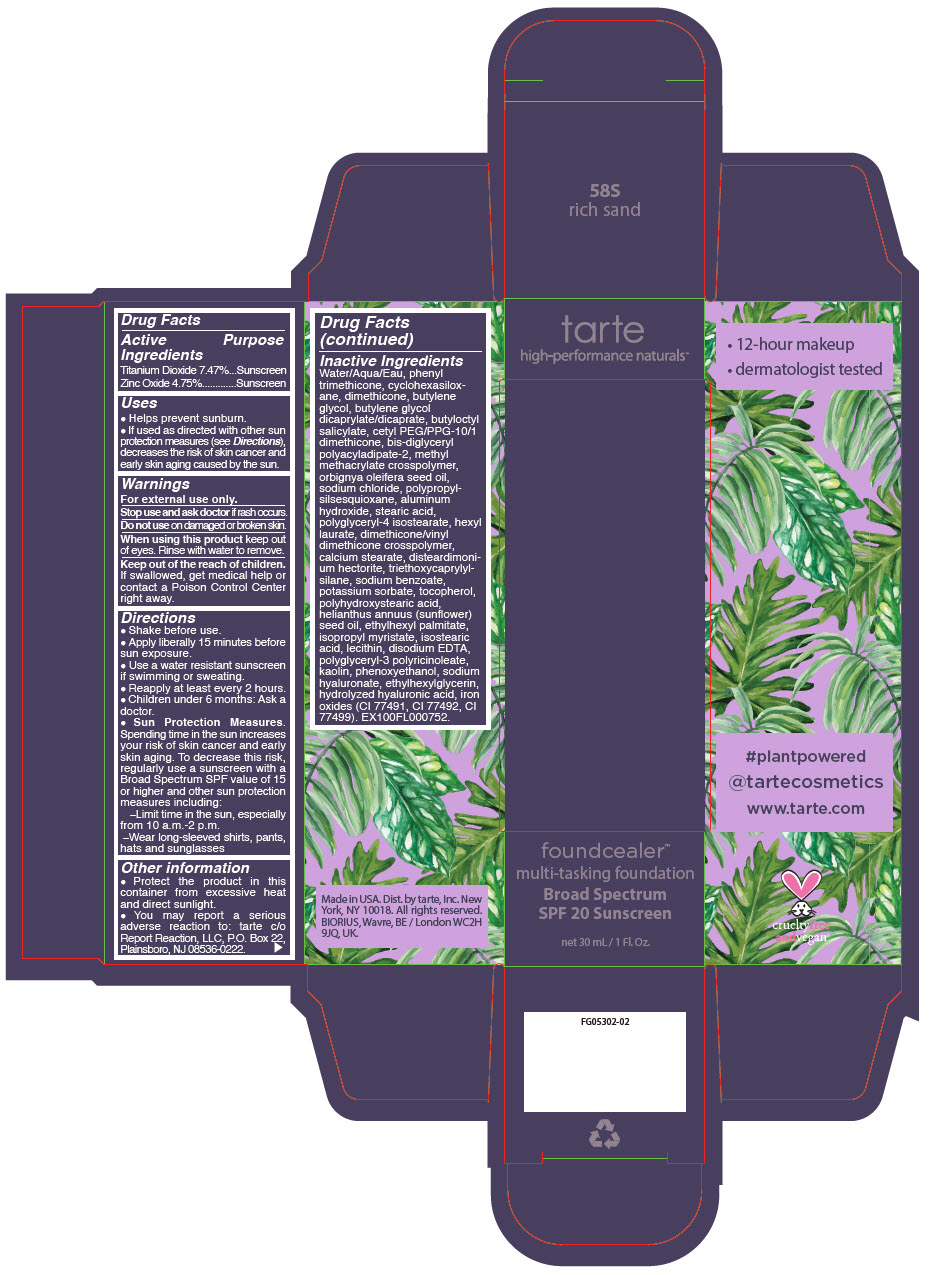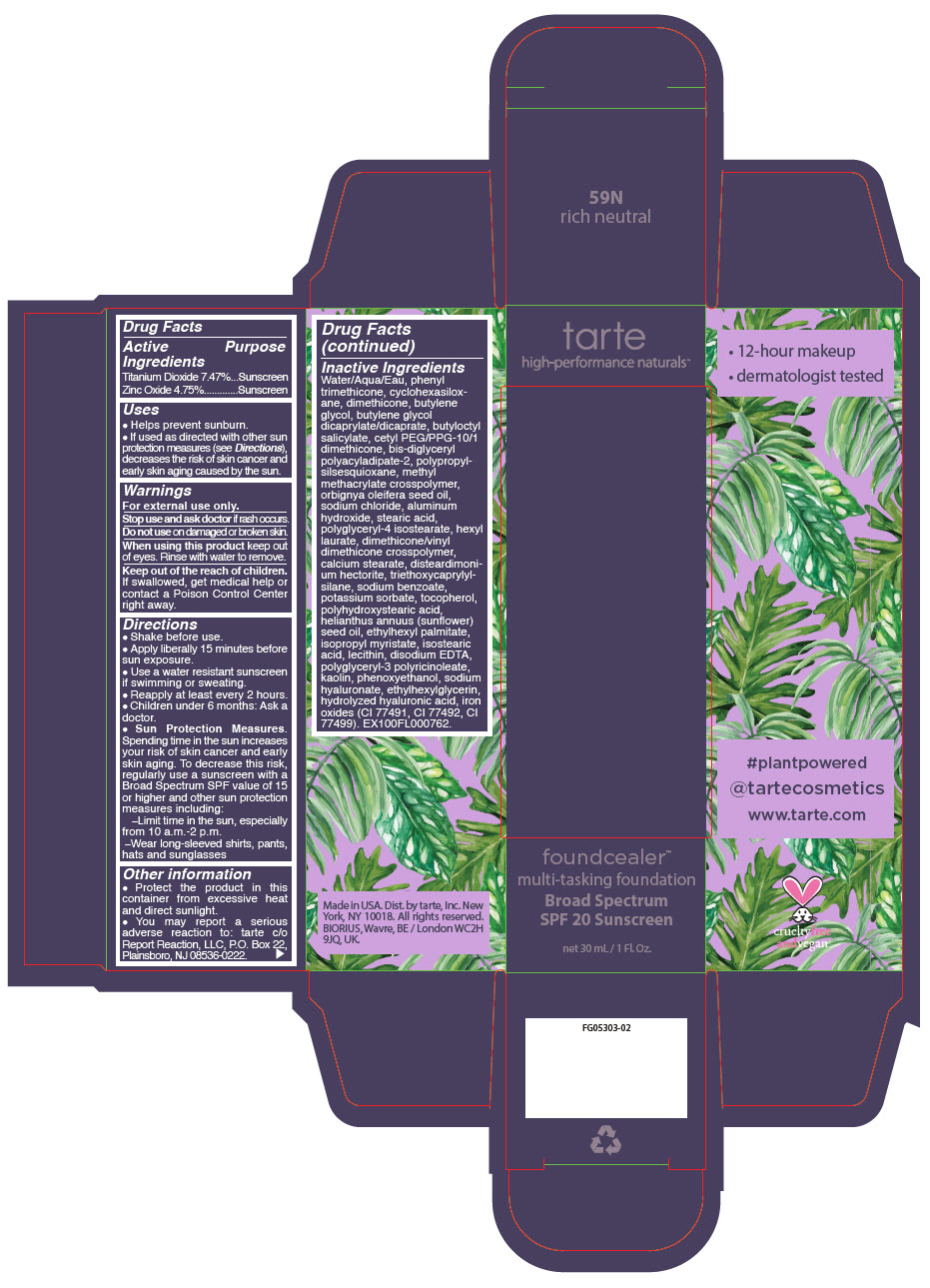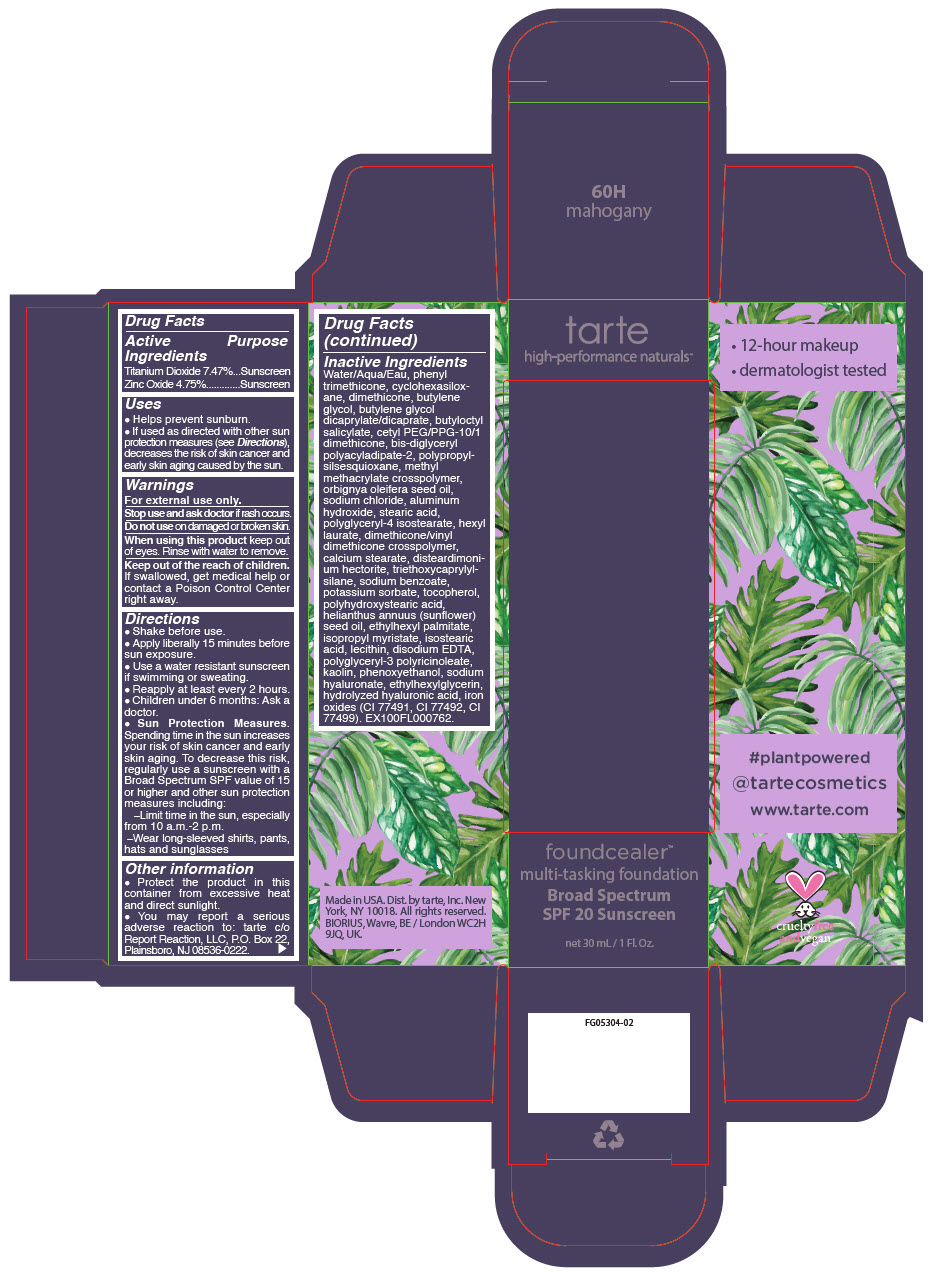 DRUG LABEL: foundcealer multi-tasking foundation Broad Spectrum SPF 20 Sunscreen 
NDC: 51060-197 | Form: LIQUID
Manufacturer: Tarte, Inc.
Category: otc | Type: HUMAN OTC DRUG LABEL
Date: 20241220

ACTIVE INGREDIENTS: Titanium Dioxide 74.7 mg/1 mL; Zinc Oxide 47.5 mg/1 mL
INACTIVE INGREDIENTS: WATER; PHENYL TRIMETHICONE; BUTYLENE GLYCOL; DIMETHICONE; BUTYLENE GLYCOL DICAPRYLATE/DICAPRATE; BUTYLOCTYL SALICYLATE; CYCLOMETHICONE 6; CETYL PEG/PPG-10/1 DIMETHICONE (HLB 2); BIS-DIGLYCERYL POLYACYLADIPATE-2; ALUMINUM HYDROXIDE; METHYL METHACRYLATE/GLYCOL DIMETHACRYLATE CROSSPOLYMER; BABASSU OIL; SODIUM CHLORIDE; STEARIC ACID; POLYGLYCERYL-4 ISOSTEARATE; HEXYL LAURATE; DIMETHICONE/VINYL DIMETHICONE CROSSPOLYMER (SOFT PARTICLE); CALCIUM STEARATE; DISTEARDIMONIUM HECTORITE; TRIETHOXYCAPRYLYLSILANE; SODIUM BENZOATE; POTASSIUM SORBATE; TOCOPHEROL; POLYHYDROXYSTEARIC ACID (2300 MW); SUNFLOWER OIL; ETHYLHEXYL PALMITATE; ISOPROPYL MYRISTATE; ISOSTEARIC ACID; SOYBEAN LECITHIN; EDETATE DISODIUM ANHYDROUS; CYCLOMETHICONE 5; POLYGLYCERYL-3 PENTARICINOLEATE; KAOLIN; CYCLOMETHICONE 4; PHENOXYETHANOL; HYALURONATE SODIUM; ETHYLHEXYLGLYCERIN; HYALURONIC ACID; FERRIC OXIDE YELLOW; FERRIC OXIDE RED; FERROSOFERRIC OXIDE

foundcealer™ multi-tasking foundation Broad Spectrum SPF 20 Sunscreen

Drug Facts

ACTIVE INGREDIENT

Active Ingredients | Purpose
Titanium Dioxide 7.47% | Sunscreen
Zinc Oxide 4.75% | Sunscreen

Uses

- Helps prevent sunburn.
- If used as directed with other sun protection measures (see Directions), decreases the risk of skin cancer and early skin aging caused by the sun.

Warnings

For external use only.

Stop use and ask doctor if rash occurs.

Do not use on damaged or broken skin.

When using this product keep out of eyes. Rinse with water to remove.

KEEP OUT OF REACH OF CHILDREN

Keep out of the reach of children. If swallowed, get medical help or contact a Poison Control Center right away.

Directions

- Shake before use.
- Apply liberally 15 minutes before sun exposure.
- Use a water resistant sunscreen if swimming or sweating.
- Reapply at least every 2 hours.
- Children under 6 months: Ask a doctor.
- Sun Protection Measures. Spending time in the sun increases your risk of skin cancer and early skin aging. To decrease this risk, regularly use a sunscreen with a Broad Spectrum SPF value of 15 or higher and other sun protection measures including:
  - Limit time in the sun, especially from 10 a.m.-2 p.m.
  - Wear long-sleeved shirts, pants, hats and sunglasses

Other information

- Protect the product in this container from excessive heat and direct sunlight.
- You may report a serious adverse reaction to: tarte c/o Report Reaction, LLC, P.O. Box 22, Plainsboro, NJ 08536-0222.

Inactive Ingredients

Water/Aqua/Eau, phenyl trimethicone, butylene glycol, dimethicone, butylene glycol dicaprylate/dicaprate, butyloctyl salicylate, cyclohexasiloxane, cetyl PEG/PPG-10/1 dimethicone, bis-diglyceryl polyacyladipate-2, aluminum hydroxide, methyl methacrylate crosspolymer, orbignya oleifera seed oil, sodium chloride, polypropylsilsesquioxane, stearic acid, polyglyceryl-4 isostearate, hexyl laurate, dimethicone/vinyl dimethicone crosspolymer, calcium stearate, disteardimonium hectorite, triethoxycaprylylsilane, sodium benzoate, potassium sorbate, tocopherol, polyhydroxystearic acid, helianthus annuus (sunflower) seed oil, ethylhexyl palmitate, isopropyl myristate, isostearic acid, lecithin, disodium EDTA, polyglyceryl-3 polyricinoleate, kaolin, phenoxyethanol, sodium hyaluronate, ethylhexylglycerin, hydrolyzed hyaluronic acid, titanium dioxide (CI 77891), iron oxides (CI 77491, CI 77492, CI 77499). EX100FL000712.

Dist. by tarte, Inc.
New York, NY 10018.

PRINCIPAL DISPLAY PANEL - 30 mL Bottle Carton - 8B - porcelain beige

tarte
high-performance naturals™

foundcealer™
multi-tasking foundation
Broad Spectrum
SPF 20 Sunscreen

net 30 mL / 1 Fl. Oz.

PRINCIPAL DISPLAY PANEL - 30 mL Bottle Carton - 13N - fair neutral

tarte
high-performance naturals™

foundcealer™
multi-tasking foundation
Broad Spectrum
SPF 20 Sunscreen

net 30 mL / 1 Fl. Oz.

PRINCIPAL DISPLAY PANEL - 30 mL Bottle Carton - 14S - fair sand

tarte
high-performance naturals™

foundcealer™
multi-tasking foundation
Broad Spectrum
SPF 20 Sunscreen

net 30 mL / 1 Fl. Oz.

PRINCIPAL DISPLAY PANEL - 30 mL Bottle Carton - 16B - fair-light beige

tarte
high-performance naturals™

foundcealer™
multi-tasking foundation
Broad Spectrum
SPF 20 Sunscreen

net 30 mL / 1 Fl. Oz.

PRINCIPAL DISPLAY PANEL - 30 mL Bottle Carton - 16S - fair-light sand

tarte
high-performance naturals™

foundcealer™
multi-tasking foundation
Broad Spectrum
SPF 20 Sunscreen

net 30 mL / 1 Fl. Oz.

PRINCIPAL DISPLAY PANEL - 30 mL Bottle Carton - 16N - fair-light neutral

tarte
high-performance naturals™

foundcealer™
multi-tasking foundation
Broad Spectrum
SPF 20 Sunscreen

net 30 mL / 1 Fl. Oz.

PRINCIPAL DISPLAY PANEL - 30 mL Bottle Carton - 22S - light sand

tarte
high-performance naturals™

foundcealer™
multi-tasking foundation
Broad Spectrum
SPF 20 Sunscreen

net 30 mL / 1 Fl. Oz.

PRINCIPAL DISPLAY PANEL - 30 mL Bottle Carton - 22N - light neutral

tarte
high-performance naturals™

foundcealer™
multi-tasking foundation
Broad Spectrum
SPF 20 Sunscreen

net 30 mL / 1 Fl. Oz.

PRINCIPAL DISPLAY PANEL - 30 mL Bottle Carton - 22B - light beige

tarte
high-performance naturals™

foundcealer™
multi-tasking foundation
Broad Spectrum
SPF 20 Sunscreen

net 30 mL / 1 Fl. Oz.

PRINCIPAL DISPLAY PANEL - 30 mL Bottle Carton - 24G - light golden

tarte
high-performance naturals™

foundcealer™
multi-tasking foundation
Broad Spectrum
SPF 20 Sunscreen

net 30 mL / 1 Fl. Oz.

PRINCIPAL DISPLAY PANEL - 30 mL Bottle Carton - 27S - light-medium sand

tarte
high-performance naturals™

foundcealer™
multi-tasking foundation
Broad Spectrum
SPF 20 Sunscreen

net 30 mL / 1 Fl. Oz.

PRINCIPAL DISPLAY PANEL - 30 mL Bottle Carton - 27N - light-medium neutral

tarte
high-performance naturals™

foundcealer™
multi-tasking foundation
Broad Spectrum
SPF 20 Sunscreen

net 30 mL / 1 Fl. Oz.

PRINCIPAL DISPLAY PANEL - 30 mL Bottle Carton - 29H - light-medium honey

tarte
high-performance naturals™

foundcealer™
multi-tasking foundation
Broad Spectrum
SPF 20 Sunscreen

net 30 mL / 1 Fl. Oz.

PRINCIPAL DISPLAY PANEL - 30 mL Bottle Carton - 34S - medium sand

tarte
high-performance naturals™

foundcealer™
multi-tasking foundation
Broad Spectrum
SPF 20 Sunscreen

net 30 mL / 1 Fl. Oz.

PRINCIPAL DISPLAY PANEL - 30 mL Bottle Carton - 34N - medium neutral

tarte
high-performance naturals™

foundcealer™
multi-tasking foundation
Broad Spectrum
SPF 20 Sunscreen

net 30 mL / 1 Fl. Oz.

PRINCIPAL DISPLAY PANEL - 30 mL Bottle Carton - 35G - medium golden

tarte
high-performance naturals™

foundcealer™
multi-tasking foundation
Broad Spectrum
SPF 20 Sunscreen

net 30 mL / 1 Fl. Oz.

PRINCIPAL DISPLAY PANEL - 30 mL Bottle Carton - 36H - medium-tan honey

tarte
high-performance naturals™

foundcealer™
multi-tasking foundation
Broad Spectrum
SPF 20 Sunscreen

net 30 mL / 1 Fl. Oz.

PRINCIPAL DISPLAY PANEL - 30 mL Bottle Carton - 36N - medium-tan neutral

tarte
high-performance naturals™

foundcealer™
multi-tasking foundation
Broad Spectrum
SPF 20 Sunscreen

net 30 mL / 1 Fl. Oz.

PRINCIPAL DISPLAY PANEL - 30 mL Bottle Carton - 38S - medium-tan sand

tarte
high-performance naturals™

foundcealer™
multi-tasking foundation
Broad Spectrum
SPF 20 Sunscreen

net 30 mL / 1 Fl. Oz.

PRINCIPAL DISPLAY PANEL - 30 mL Bottle Carton - 42N - tan neutral

tarte
high-performance naturals™

foundcealer™
multi-tasking foundation
Broad Spectrum
SPF 20 Sunscreen

net 30 mL / 1 Fl. Oz.

PRINCIPAL DISPLAY PANEL - 30 mL Bottle Carton - 44H - tan honey

tarte
high-performance naturals™

foundcealer™
multi-tasking foundation
Broad Spectrum
SPF 20 Sunscreen

net 30 mL / 1 Fl. Oz.

PRINCIPAL DISPLAY PANEL - 30 mL Bottle Carton - 44S - tan sand

tarte
high-performance naturals™

foundcealer™
multi-tasking foundation
Broad Spectrum
SPF 20 Sunscreen

net 30 mL / 1 Fl. Oz.

PRINCIPAL DISPLAY PANEL - 30 mL Bottle Carton - 48S - tan-deep sand

tarte
high-performance naturals™

foundcealer™
multi-tasking foundation
Broad Spectrum
SPF 20 Sunscreen

net 30 mL / 1 Fl. Oz.

PRINCIPAL DISPLAY PANEL - 30 mL Bottle Carton - 49H - tan-deep honey

tarte
high-performance naturals™

foundcealer™
multi-tasking foundation
Broad Spectrum
SPF 20 Sunscreen

net 30 mL / 1 Fl. Oz.

PRINCIPAL DISPLAY PANEL - 30 mL Bottle Carton - 50S - deep sand

tarte
high-performance naturals™

foundcealer™
multi-tasking foundation
Broad Spectrum
SPF 20 Sunscreen

net 30 mL / 1 Fl. Oz.

PRINCIPAL DISPLAY PANEL - 30 mL Bottle Carton - 52N - deep neutral

tarte
high-performance naturals™

foundcealer™
multi-tasking foundation
Broad Spectrum
SPF 20 Sunscreen

net 30 mL / 1 Fl. Oz.

PRINCIPAL DISPLAY PANEL - 30 mL Bottle Carton - 54H - deep honey

tarte
high-performance naturals™

foundcealer™
multi-tasking foundation
Broad Spectrum
SPF 20 Sunscreen

net 30 mL / 1 Fl. Oz.

PRINCIPAL DISPLAY PANEL - 30 mL Bottle Carton - 58S - rich sand

tarte
high-performance naturals™

foundcealer™
multi-tasking foundation
Broad Spectrum
SPF 20 Sunscreen

net 30 mL / 1 Fl. Oz.

PRINCIPAL DISPLAY PANEL - 30 mL Bottle Carton - 59N - rich neutral

tarte
high-performance naturals™

foundcealer™
multi-tasking foundation
Broad Spectrum
SPF 20 Sunscreen

net 30 mL / 1 Fl. Oz.

PRINCIPAL DISPLAY PANEL - 30 mL Bottle Carton - 60H - mahogany

tarte
high-performance naturals™

foundcealer™
multi-tasking foundation
Broad Spectrum
SPF 20 Sunscreen

net 30 mL / 1 Fl. Oz.